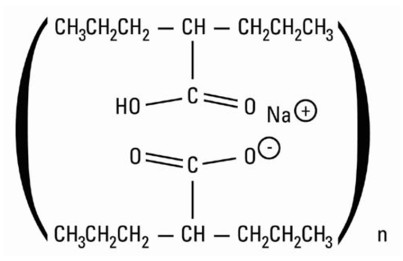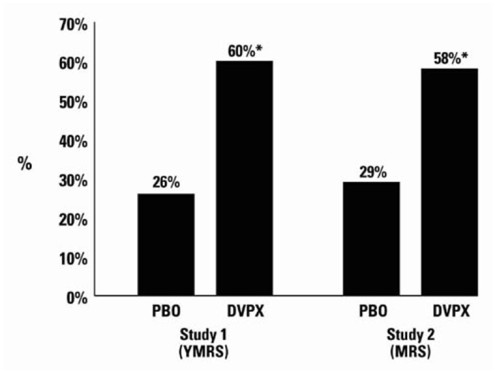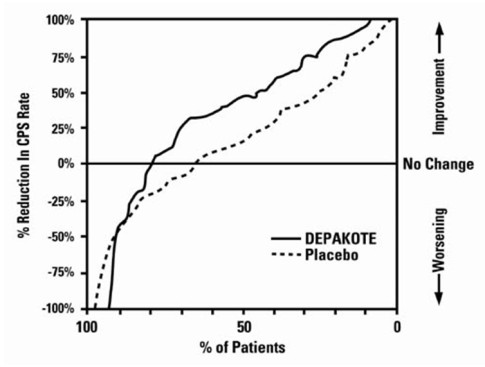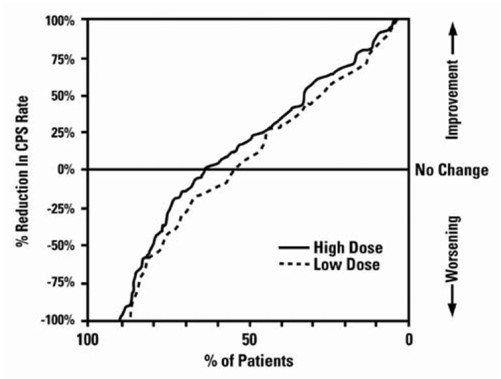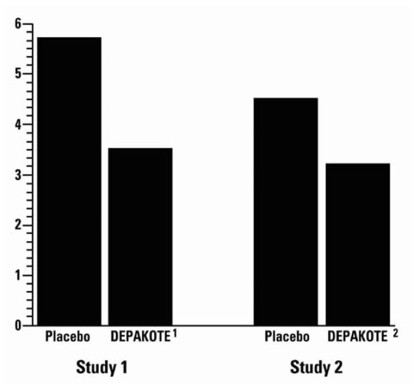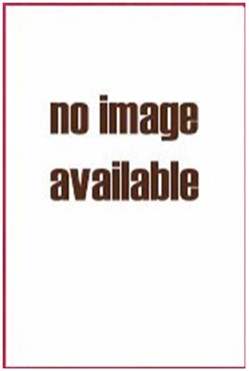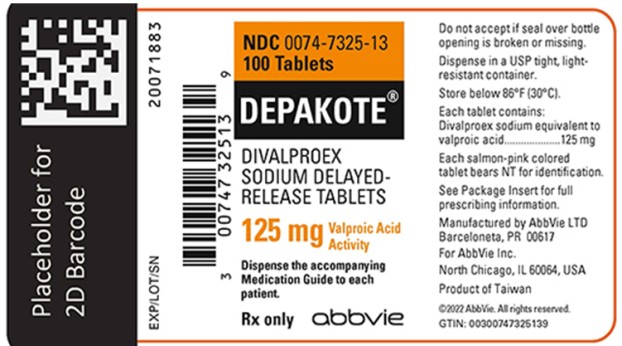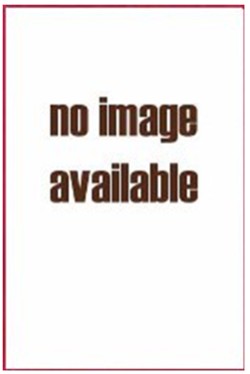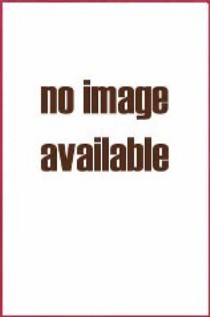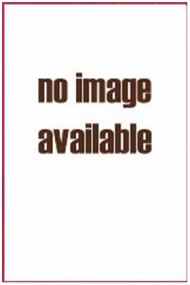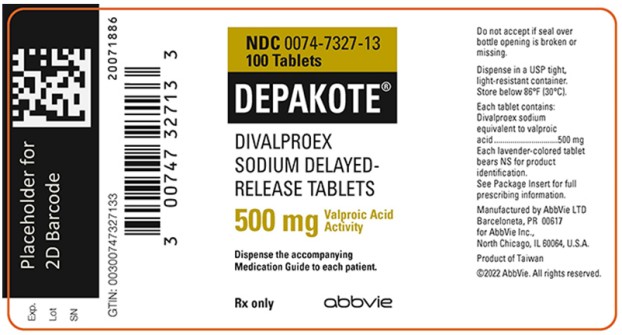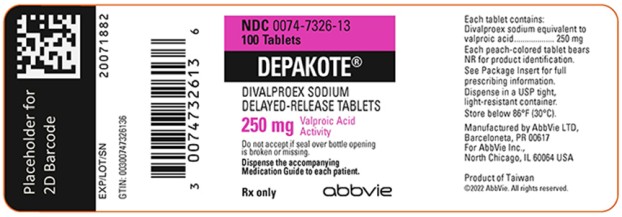 DRUG LABEL: Depakote
NDC: 0074-6212 | Form: TABLET, DELAYED RELEASE
Manufacturer: AbbVie Inc.
Category: prescription | Type: HUMAN PRESCRIPTION DRUG LABEL
Date: 20250501

ACTIVE INGREDIENTS: DIVALPROEX SODIUM 125 mg/1 1
INACTIVE INGREDIENTS: DIACETYLATED MONOGLYCERIDES; POVIDONE, UNSPECIFIED; STARCH, CORN; SILICON DIOXIDE; TALC; TITANIUM DIOXIDE; VANILLIN; FD&C BLUE NO. 1; FD&C RED NO. 40

HIGHLIGHTS OF PRESCRIBING INFORMATION

These highlights do not include all the information needed to use Depakote safely and effectively. See full prescribing information for Depakote.
Depakote (divalproex sodium) delayed-release tablets, for oral use
Initial U.S. Approval: 1983

RECENT MAJOR CHANGES

Contraindications (4) | 5/2025
Warnings and Precautions (5.13, 5.14) | 5/2025

WARNING: LIFE THREATENING ADVERSE REACTIONS

See full prescribing information for complete boxed warning.

- Hepatotoxicity, including fatalities, usually during the first 6 months of treatment. Children under the age of two years and patients with mitochondrial disorders are at higher risk. Monitor patients closely, and perform serum liver testing prior to therapy and at frequent intervals thereafter (5.1)
- Fetal Risk, particularly neural tube defects, other major malformations, and decreased IQ (5.2, 5.3, 5.4)
- Pancreatitis, including fatal hemorrhagic cases (5.5)

1 INDICATIONS AND USAGE

Depakote is an anti-epileptic drug indicated for:

- Treatment of manic episodes associated with bipolar disorder (1.1)
- Monotherapy and adjunctive therapy of complex partial seizures and simple and complex absence seizures; adjunctive therapy in patients with multiple seizure types that include absence seizures (1.2)
- Prophylaxis of migraine headaches (1.3)

2 DOSAGE AND ADMINISTRATION

- Depakote is administered orally in divided doses. Depakote should be swallowed whole and should not be crushed or chewed (2.1, 2.2).
- Mania: Initial dose is 750 mg daily, increasing as rapidly as possible to achieve therapeutic response or desired plasma level (2.1). The maximum recommended dosage is 60 mg/kg/day (2.1, 2.2).
- Complex Partial Seizures: Start at 10 to 15 mg/kg/day, increasing at 1 week intervals by 5 to 10 mg/kg/day to achieve optimal clinical response; if response is not satisfactory, check valproate plasma level; see full prescribing information for conversion to monotherapy (2.2). The maximum recommended dosage is 60 mg/kg/day (2.1, 2.2).
- Absence Seizures: Start at 15 mg/kg/day, increasing at 1 week intervals by 5 to 10 mg/kg/day until seizure control or limiting side effects (2.2). The maximum recommended dosage is 60 mg/kg/day (2.1, 2.2).
- Migraine: The recommended starting dose is 250 mg twice daily, thereafter increasing to a maximum of 1,000 mg/day as needed (2.3).

3 DOSAGE FORMS AND STRENGTHS

Tablets: 125 mg, 250 mg and 500 mg (3)

4 CONTRAINDICATIONS

- Hepatic disease or significant hepatic dysfunction (4, 5.1)
- Known mitochondrial disorders caused by mutations in mitochondrial DNA polymerase γ (POLG) (4, 5.1)
- Suspected POLG-related disorder in children under two years of age (4, 5.1)
- Known hypersensitivity to divalproex sodium, sodium valproate, or valproic acid (4, 5.12, 5.13, 5.14)
- Urea cycle disorders (4, 5.6)
- Prophylaxis of migraine headaches: Pregnant women, women of childbearing potential not using effective contraception (4, 8.1)

5 WARNINGS AND PRECAUTIONS

- Birth defects, decreased IQ, and neurodevelopmental disorders following in utero exposure: Should not be used to treat women with epilepsy or bipolar disorder who are pregnant or who plan to become pregnant or to treat a woman of childbearing potential unless other medications have failed to provide adequate symptom control or are otherwise unacceptable (5.2, 5.3, 5.4)
- Pancreatitis: Depakote should ordinarily be discontinued (5.5)
- Suicidal behavior or ideation: Antiepileptic drugs, including Depakote, increase the risk of suicidal thoughts or behavior (5.7)
- Bleeding and other hematopoietic disorders: Monitor platelet counts and coagulation tests (5.8)
- Hyperammonemia and hyperammonemic encephalopathy: Measure ammonia level if unexplained lethargy and vomiting or changes in mental status, and also with concomitant topiramate use; consider discontinuation of valproate therapy (5.6, 5.9, 5.10)
- Hypothermia: Hypothermia has been reported during valproate therapy with or without associated hyperammonemia. This adverse reaction can also occur in patients using concomitant topiramate (5.11)
- Drug Reaction with Eosinophilia and Systemic Symptoms (DRESS)/Multiorgan Hypersensitivity Reactions, serious dermatologic reactions, and angioedema: Discontinue Depakote unless an alternate etiology is established (4, 5.12, 5.13, 5.14)

6 ADVERSE REACTIONS

- Most common adverse reactions (reported ≥15% for any indication) are abdominal pain, alopecia, asthenia, diarrhea, diplopia, dizziness, headache, infection, insomnia, nausea, somnolence, thrombocytopenia, tremor, vomiting (6.1, 6.2, 6.3).
- The safety and tolerability of valproate in pediatric patients were shown to be comparable to those in adults (8.4).

To report SUSPECTED ADVERSE REACTIONS, contact AbbVie Inc. at 1-800-633-9110 or FDA at 1-800-FDA-1088 or www.fda.gov/medwatch.

7 DRUG INTERACTIONS

- Hepatic enzyme-inducing drugs (e.g., phenytoin, carbamazepine, phenobarbital, primidone, rifampin) can increase valproate clearance, while enzyme inhibitors (e.g., felbamate) can decrease valproate clearance. Therefore increased monitoring of valproate and concomitant drug concentrations and dosage adjustment are indicated whenever enzyme-inducing or inhibiting drugs are introduced or withdrawn (7.1)
- Aspirin, carbapenem antibiotics, estrogen-containing hormonal contraceptives, methotrexate: Monitoring of valproate concentrations is recommended (7.1)
- Co-administration of valproate can affect the pharmacokinetics of other drugs (e.g., diazepam, ethosuximide, lamotrigine, phenytoin) by inhibiting their metabolism or protein binding displacement (7.2)
- Patients stabilized on rufinamide should begin valproate therapy at a low dose, and titrate to clinically effective dose (7.2)
- Dosage adjustment of amitriptyline/nortriptyline, propofol, warfarin, and zidovudine may be necessary if used concomitantly with Depakote (7.2)
- Topiramate: Hyperammonemia and encephalopathy (5.10, 7.3)
- Cannabidiol: ALT and/or AST elevation (7.4)

8 USE IN SPECIFIC POPULATIONS

- Pregnancy: Depakote can cause congenital malformations including neural tube defects, decreased IQ, and neurodevelopmental disorders (5.2, 5.3, 8.1)
- Geriatric: Reduce starting dose; increase dosage more slowly; monitor fluid and nutritional intake, and somnolence (5.16, 8.5)

FULL PRESCRIBING INFORMATION

WARNING: LIFE THREATENING ADVERSE REACTIONS

Hepatotoxicity

General Population: Hepatic failure resulting in fatalities has occurred in patients receiving valproate and its derivatives. These incidents usually have occurred during the first six months of treatment. Serious or fatal hepatotoxicity may be preceded by non-specific symptoms such as malaise, weakness, lethargy, facial edema, anorexia, and vomiting. In patients with epilepsy, a loss of seizure control may also occur. Patients should be monitored closely for appearance of these symptoms. Serum liver tests should be performed prior to therapy and at frequent intervals thereafter, especially during the first six months [see Warnings and Precautions (5.1)].

Children under the age of two years are at a considerably increased risk of developing fatal hepatotoxicity, especially those on multiple anticonvulsants, those with congenital metabolic disorders, those with severe seizure disorders accompanied by mental retardation, and those with organic brain disease. When Depakote is used in this patient group, it should be used with extreme caution and as a sole agent. The benefits of therapy should be weighed against the risks. The incidence of fatal hepatotoxicity decreases considerably in progressively older patient groups.

Patients with Mitochondrial Disease: There is an increased risk of valproate-induced acute liver failure and resultant deaths in patients with hereditary neurometabolic syndromes caused by DNA mutations of the mitochondrial DNA Polymerase γ (POLG) gene (e.g., Alpers Huttenlocher Syndrome). Depakote is contraindicated in patients known to have mitochondrial disorders caused by POLG mutations and children under two years of age who are clinically suspected of having a mitochondrial disorder [see Contraindications (4)]. In patients over two years of age who are clinically suspected of having a hereditary mitochondrial disease, Depakote should only be used after other anticonvulsants have failed. This older group of patients should be closely monitored during treatment with Depakote for the development of acute liver injury with regular clinical assessments and serum liver testing. POLG mutation screening should be performed in accordance with current clinical practice [see Warnings and Precautions (5.1)].

Fetal Risk

Valproate can cause major congenital malformations, particularly neural tube defects (e.g., spina bifida). In addition, valproate can cause decreased IQ scores and neurodevelopmental disorders following in utero exposure.

Valproate is therefore contraindicated for prophylaxis of migraine headaches in pregnant women and in women of childbearing potential who are not using effective contraception [see Contraindications (4)]. Valproate should not be used to treat women with epilepsy or bipolar disorder who are pregnant or who plan to become pregnant unless other medications have failed to provide adequate symptom control or are otherwise unacceptable.

Valproate should not be administered to a woman of childbearing potential unless other medications have failed to provide adequate symptom control or are otherwise unacceptable. In such situations, effective contraception should be used [see Warnings and Precautions (5.2, 5.3, 5.4)].

A Medication Guide describing the risks of valproate is available for patients [see Patient Counseling Information (17)].

Pancreatitis

Cases of life-threatening pancreatitis have been reported in both children and adults receiving valproate. Some of the cases have been described as hemorrhagic with a rapid progression from initial symptoms to death. Cases have been reported shortly after initial use as well as after several years of use. Patients and guardians should be warned that abdominal pain, nausea, vomiting, and/or anorexia can be symptoms of pancreatitis that require prompt medical evaluation. If pancreatitis is diagnosed, valproate should ordinarily be discontinued. Alternative treatment for the underlying medical condition should be initiated as clinically indicated [see Warnings and Precautions (5.5)].

1 INDICATIONS AND USAGE

1.1 Mania

Depakote (divalproex sodium) is a valproate and is indicated for the treatment of the manic episodes associated with bipolar disorder. A manic episode is a distinct period of abnormally and persistently elevated, expansive, or irritable mood. Typical symptoms of mania include pressure of speech, motor hyperactivity, reduced need for sleep, flight of ideas, grandiosity, poor judgment, aggressiveness, and possible hostility.

The efficacy of Depakote was established in 3-week trials with patients meeting DSM-III-R criteria for bipolar disorder who were hospitalized for acute mania [see Clinical Studies (14.1)].

The safety and effectiveness of Depakote for long-term use in mania, i.e., more than 3 weeks, has not been demonstrated in controlled clinical trials. Therefore, healthcare providers who elect to use Depakote for extended periods should continually reevaluate the long-term usefulness of the drug for the individual patient.

1.2 Epilepsy

Depakote is indicated as monotherapy and adjunctive therapy in the treatment of patients with complex partial seizures that occur either in isolation or in association with other types of seizures. Depakote is also indicated for use as sole and adjunctive therapy in the treatment of simple and complex absence seizures, and adjunctively in patients with multiple seizure types that include absence seizures.

Simple absence is defined as very brief clouding of the sensorium or loss of consciousness accompanied by certain generalized epileptic discharges without other detectable clinical signs. Complex absence is the term used when other signs are also present.

1.3 Migraine

Depakote is indicated for prophylaxis of migraine headaches. There is no evidence that Depakote is useful in the acute treatment of migraine headaches.

1.4 Important Limitations

Because of the risk to the fetus of decreased IQ, neurodevelopmental disorders, neural tube defects, and other major congenital malformations, which may occur very early in pregnancy, valproate should not be used to treat women with epilepsy or bipolar disorder who are pregnant or who plan to become pregnant unless other medications have failed to provide adequate symptom control or are otherwise unacceptable. Valproate should not be administered to a woman of childbearing potential unless other medications have failed to provide adequate symptom control or are otherwise unacceptable [see Warnings and Precautions (5.2, 5.3, 5.4), Use in Specific Populations (8.1), and Patient Counseling Information (17)].

For prophylaxis of migraine headaches, Depakote is contraindicated in women who are pregnant and in women of childbearing potential who are not using effective contraception [see Contraindications (4)].

2 DOSAGE AND ADMINISTRATION

Depakote tablets are intended for oral administration. Depakote tablets should be swallowed whole and should not be crushed or chewed.

Patients should be informed to take Depakote every day as prescribed. If a dose is missed it should be taken as soon as possible, unless it is almost time for the next dose. If a dose is skipped, the patient should not double the next dose.

2.1 Mania

Depakote tablets are administered orally. The recommended initial dose is 750 mg daily in divided doses. The dose should be increased as rapidly as possible to achieve the lowest therapeutic dose which produces the desired clinical effect or the desired range of plasma concentrations. In placebo-controlled clinical trials of acute mania, patients were dosed to a clinical response with a trough plasma concentration between 50 and 125 mcg/mL. Maximum concentrations were generally achieved within 14 days. The maximum recommended dosage is 60 mg/kg/day.

There is no body of evidence available from controlled trials to guide a clinician in the longer term management of a patient who improves during Depakote treatment of an acute manic episode. While it is generally agreed that pharmacological treatment beyond an acute response in mania is desirable, both for maintenance of the initial response and for prevention of new manic episodes, there are no data to support the benefits of Depakote in such longer-term treatment. Although there are no efficacy data that specifically address longer-term antimanic treatment with Depakote, the safety of Depakote in long-term use is supported by data from record reviews involving approximately 360 patients treated with Depakote for greater than 3 months.

2.2 Epilepsy

Depakote tablets are administered orally. Depakote is indicated as monotherapy and adjunctive therapy in complex partial seizures in adults and pediatric patients down to the age of 10 years, and in simple and complex absence seizures. As the Depakote dosage is titrated upward, concentrations of clonazepam, diazepam, ethosuximide, lamotrigine, tolbutamide, phenobarbital, carbamazepine, and/or phenytoin may be affected [see Drug Interactions (7.2)].

Complex Partial Seizures

For adults and children 10 years of age or older.

Monotherapy (Initial Therapy)

Depakote has not been systematically studied as initial therapy. Patients should initiate therapy at 10 to 15 mg/kg/day. The dosage should be increased by 5 to 10 mg/kg/week to achieve optimal clinical response. Ordinarily, optimal clinical response is achieved at daily doses below 60 mg/kg/day. If satisfactory clinical response has not been achieved, plasma levels should be measured to determine whether or not they are in the usually accepted therapeutic range (50 to 100 mcg/mL). No recommendation regarding the safety of valproate for use at doses above 60 mg/kg/day can be made.

The probability of thrombocytopenia increases significantly at total trough valproate plasma concentrations above 110 mcg/mL in females and 135 mcg/mL in males. The benefit of improved seizure control with higher doses should be weighed against the possibility of a greater incidence of adverse reactions.

Conversion to Monotherapy

Patients should initiate therapy at 10 to 15 mg/kg/day. The dosage should be increased by 5 to 10 mg/kg/week to achieve optimal clinical response. Ordinarily, optimal clinical response is achieved at daily doses below 60 mg/kg/day. If satisfactory clinical response has not been achieved, plasma levels should be measured to determine whether or not they are in the usually accepted therapeutic range (50-100 mcg/mL). No recommendation regarding the safety of valproate for use at doses above 60 mg/kg/day can be made. Concomitant antiepilepsy drug (AED) dosage can ordinarily be reduced by approximately 25% every 2 weeks. This reduction may be started at initiation of Depakote therapy, or delayed by 1 to 2 weeks if there is a concern that seizures are likely to occur with a reduction. The speed and duration of withdrawal of the concomitant AED can be highly variable, and patients should be monitored closely during this period for increased seizure frequency.

Adjunctive Therapy

Depakote may be added to the patient's regimen at a dosage of 10 to 15 mg/kg/day. The dosage may be increased by 5 to 10 mg/kg/week to achieve optimal clinical response. Ordinarily, optimal clinical response is achieved at daily doses below 60 mg/kg/day. If satisfactory clinical response has not been achieved, plasma levels should be measured to determine whether or not they are in the usually accepted therapeutic range (50 to 100 mcg/mL). No recommendation regarding the safety of valproate for use at doses above 60 mg/kg/day can be made. If the total daily dose exceeds 250 mg, it should be given in divided doses.

In a study of adjunctive therapy for complex partial seizures in which patients were receiving either carbamazepine or phenytoin in addition to valproate, no adjustment of carbamazepine or phenytoin dosage was needed [see Clinical Studies (14.2)]. However, since valproate may interact with these or other concurrently administered AEDs as well as other drugs, periodic plasma concentration determinations of concomitant AEDs are recommended during the early course of therapy [see Drug Interactions (7)].

Simple and Complex Absence Seizures

The recommended initial dose is 15 mg/kg/day, increasing at one week intervals by 5 to 10 mg/kg/day until seizures are controlled or side effects preclude further increases. The maximum recommended dosage is 60 mg/kg/day. If the total daily dose exceeds 250 mg, it should be given in divided doses.

A good correlation has not been established between daily dose, serum concentrations, and therapeutic effect. However, therapeutic valproate serum concentrations for most patients with absence seizures is considered to range from 50 to 100 mcg/mL. Some patients may be controlled with lower or higher serum concentrations [see Clinical Pharmacology (12.3)].

As the Depakote dosage is titrated upward, blood concentrations of phenobarbital and/or phenytoin may be affected [see Drug Interactions (7.2)].

Antiepilepsy drugs should not be abruptly discontinued in patients in whom the drug is administered to prevent major seizures because of the strong possibility of precipitating status epilepticus with attendant hypoxia and threat to life.

In epileptic patients previously receiving valproic acid therapy, Depakote tablets should be initiated at the same daily dose and dosing schedule. After the patient is stabilized on Depakote tablets, a dosing schedule of two or three times a day may be elected in selected patients.

2.3 Migraine

Depakote is indicated for prophylaxis of migraine headaches in adults.

Depakote tablets are administered orally. The recommended starting dose is 250 mg twice daily. Some patients may benefit from doses up to 1,000 mg/day. In the clinical trials, there was no evidence that higher doses led to greater efficacy.

2.4 General Dosing Advice

Dosing in Elderly Patients

Due to a decrease in unbound clearance of valproate and possibly a greater sensitivity to somnolence in the elderly, the starting dose should be reduced in these patients. Dosage should be increased more slowly and with regular monitoring for fluid and nutritional intake, dehydration, somnolence, and other adverse reactions. Dose reductions or discontinuation of valproate should be considered in patients with decreased food or fluid intake and in patients with excessive somnolence. The ultimate therapeutic dose should be achieved on the basis of both tolerability and clinical response [see Warnings and Precautions (5.16), Use in Specific Populations (8.5), and Clinical Pharmacology (12.3)].

Dose-Related Adverse Reactions

The frequency of adverse effects (particularly elevated liver enzymes and thrombocytopenia) may be dose-related. The probability of thrombocytopenia appears to increase significantly at total valproate concentrations of ≥ 110 mcg/mL (females) or ≥ 135 mcg/mL (males) [see Warnings and Precautions (5.8)]. The benefit of improved therapeutic effect with higher doses should be weighed against the possibility of a greater incidence of adverse reactions.

G.I. Irritation

Patients who experience G.I. irritation may benefit from administration of the drug with food or by slowly building up the dose from an initial low level.

2.5 Dosing in Patients Taking Rufinamide

Patients stabilized on rufinamide before being prescribed valproate should begin valproate therapy at a low dose, and titrate to a clinically effective dose [see Drug Interactions (7.2)].

3 DOSAGE FORMS AND STRENGTHS

Depakote tablets (divalproex sodium delayed-release tablets) are supplied as:

- 125 mg salmon pink-colored tablets with the “a” logo and the code NT
- 125 mg salmon pink-colored tablets with the code NT
- 250 mg peach-colored tablets with the “a” logo and the code NR
- 250 mg peach-colored tablets with the code NR
- 500 mg lavender-colored tablets with the “a” logo and the code NS
- 500 mg lavender-colored tablets with the code NS

4 CONTRAINDICATIONS

Depakote is contraindicated in patients:

• with hepatic disease or significant hepatic dysfunction [see Warnings and Precautions (5.1)].

• known to have mitochondrial disorders caused by mutations in mitochondrial DNA polymerase γ (POLG; e.g., Alpers-Huttenlocher Syndrome) and children under two years of age who are suspected of having a POLG-related disorder [see Warnings and Precautions (5.1)].

• with known hypersensitivity to divalproex sodium, sodium valproate, or valproic acid. Reactions have included multiorgan hypersensitivity, serious dermatologic reactions, and angioedema [see Warnings and Precautions (5.12, 5.13, 5.14)].

• with known urea cycle disorders [see Warnings and Precautions (5.6)].

• being treated for prophylaxis of migraine headaches who are pregnant or in women of childbearing potential who are not using effective contraception [see Warnings and Precautions (5.2, 5.3, 5.4) and Use in Specific Populations (8.1)].

5 WARNINGS AND PRECAUTIONS

5.1 Hepatotoxicity

General Information on Hepatotoxicity

Hepatic failure resulting in fatalities has occurred in patients receiving valproate. These incidents usually have occurred during the first six months of treatment. Serious or fatal hepatotoxicity may be preceded by non-specific symptoms such as malaise, weakness, lethargy, facial edema, anorexia, and vomiting. In patients with epilepsy, a loss of seizure control may also occur. Patients should be monitored closely for appearance of these symptoms. Serum liver tests should be performed prior to therapy and at frequent intervals thereafter, especially during the first six months of valproate therapy. However, healthcare providers should not rely totally on serum biochemistry since these tests may not be abnormal in all instances, but should also consider the results of careful interim medical history and physical examination.

Caution should be observed when administering valproate products to patients with a prior history of hepatic disease. Patients on multiple anticonvulsants, children, those with congenital metabolic disorders, those with severe seizure disorders accompanied by mental retardation, and those with organic brain disease may be at particular risk. See below, “Patients with Known or Suspected Mitochondrial Disease.”

Experience has indicated that children under the age of two years are at a considerably increased risk of developing fatal hepatotoxicity, especially those with the aforementioned conditions. When Depakote is used in this patient group, it should be used with extreme caution and as a sole agent. The benefits of therapy should be weighed against the risks. In progressively older patient groups experience in epilepsy has indicated that the incidence of fatal hepatotoxicity decreases considerably.

Patients with Known or Suspected Mitochondrial Disease

Depakote is contraindicated in patients known to have mitochondrial disorders caused by POLG mutations and children under two years of age who are clinically suspected of having a mitochondrial disorder [see Contraindications (4)]. Valproate-induced acute liver failure and liver-related deaths have been reported in patients with hereditary neurometabolic syndromes caused by mutations in the gene for mitochondrial DNA polymerase γ (POLG) (e.g., Alpers-Huttenlocher Syndrome) at a higher rate than those without these syndromes. Most of the reported cases of liver failure in patients with these syndromes have been identified in children and adolescents.

POLG-related disorders should be suspected in patients with a family history or suggestive symptoms of a POLG-related disorder, including but not limited to unexplained encephalopathy, refractory epilepsy (focal, myoclonic), status epilepticus at presentation, developmental delays, psychomotor regression, axonal sensorimotor neuropathy, myopathy cerebellar ataxia, ophthalmoplegia, or complicated migraine with occipital aura. POLG mutation testing should be performed in accordance with current clinical practice for the diagnostic evaluation of such disorders. The A467T and W748S mutations are present in approximately 2/3 of patients with autosomal recessive POLG-related disorders.

In patients over two years of age who are clinically suspected of having a hereditary mitochondrial disease, Depakote should only be used after other anticonvulsants have failed. This older group of patients should be closely monitored during treatment with Depakote for the development of acute liver injury with regular clinical assessments and serum liver test monitoring.

The drug should be discontinued immediately in the presence of significant hepatic dysfunction, suspected or apparent. In some cases, hepatic dysfunction has progressed in spite of discontinuation of drug [see Boxed Warning and Contraindications (4)].

5.2 Structural Birth Defects

Valproate can cause fetal harm when administered to a pregnant woman. Pregnancy registry data show that maternal valproate use can cause neural tube defects and other structural abnormalities (e.g., craniofacial defects, cardiovascular malformations, hypospadias, limb malformations). The rate of congenital malformations among babies born to mothers using valproate is about four times higher than the rate among babies born to epileptic mothers using other anti-seizure monotherapies. Evidence suggests that folic acid supplementation prior to conception and during the first trimester of pregnancy decreases the risk for congenital neural tube defects in the general population [see Use in Specific Populations (8.1)].

5.3 Decreased IQ Following in utero Exposure

Valproate can cause decreased IQ scores following in utero exposure. Published epidemiological studies have indicated that children exposed to valproate in utero have lower cognitive test scores than children exposed in utero to either another antiepileptic drug or to no antiepileptic drugs. The largest of these studies^1 is a prospective cohort study conducted in the United States and United Kingdom that found that children with prenatal exposure to valproate (n=62) had lower IQ scores at age 6 (97 [95% C.I. 94-101]) than children with prenatal exposure to the other antiepileptic drug monotherapy treatments evaluated: lamotrigine (108 [95% C.I. 105–110]), carbamazepine (105 [95% C.I. 102–108]), and phenytoin (108 [95% C.I. 104–112]). It is not known when during pregnancy cognitive effects in valproate-exposed children occur. Because the women in this study were exposed to antiepileptic drugs throughout pregnancy, whether the risk for decreased IQ was related to a particular time period during pregnancy could not be assessed.

Although all of the available studies have methodological limitations, the weight of the evidence supports the conclusion that valproate exposure in utero can cause decreased IQ in children.

In animal studies, offspring with prenatal exposure to valproate had malformations similar to those seen in humans and demonstrated neurobehavioral deficits [see Use in Specific Populations (8.1)].

5.4 Use in Women of Childbearing Potential

Because of the risk to the fetus of decreased IQ, neurodevelopmental disorders, and major congenital malformations (including neural tube defects), which may occur very early in pregnancy, valproate should not be administered to a woman of childbearing potential unless other medications have failed to provide adequate symptom control or are otherwise unacceptable. This is especially important when valproate use is considered for a condition not usually associated with permanent injury or death such as prophylaxis of migraine headaches [see Contraindications (4)]. Women should use effective contraception while using valproate.

Women of childbearing potential should be counseled regularly regarding the relative risks and benefits of valproate use during pregnancy. This is especially important for women planning a pregnancy and for girls at the onset of puberty; alternative therapeutic options should be considered for these patients [see Boxed Warning and Use in Specific Populations (8.1)].

To prevent major seizures, valproate should not be discontinued abruptly, as this can precipitate status epilepticus with resulting maternal and fetal hypoxia and threat to life.

Evidence suggests that folic acid supplementation prior to conception and during the first trimester of pregnancy decreases the risk for congenital neural tube defects in the general population. It is not known whether the risk of neural tube defects or decreased IQ in the offspring of women receiving valproate is reduced by folic acid supplementation. Dietary folic acid supplementation both prior to conception and during pregnancy should be routinely recommended for patients using valproate.

5.5 Pancreatitis

Cases of life-threatening pancreatitis have been reported in both children and adults receiving valproate. Some of the cases have been described as hemorrhagic with rapid progression from initial symptoms to death. Some cases have occurred shortly after initial use as well as after several years of use. The rate based upon the reported cases exceeds that expected in the general population and there have been cases in which pancreatitis recurred after rechallenge with valproate. In clinical trials, there were 2 cases of pancreatitis without alternative etiology in 2,416 patients, representing 1,044 patient-years experience. Patients and guardians should be warned that abdominal pain, nausea, vomiting, and/or anorexia can be symptoms of pancreatitis that require prompt medical evaluation. If pancreatitis is diagnosed, Depakote should ordinarily be discontinued. Alternative treatment for the underlying medical condition should be initiated as clinically indicated [see Boxed Warning].

5.6 Urea Cycle Disorders

Depakote is contraindicated in patients with known urea cycle disorders (UCD).

Hyperammonemic encephalopathy, sometimes fatal, has been reported following initiation of valproate therapy in patients with urea cycle disorders, a group of uncommon genetic abnormalities, particularly ornithine transcarbamylase deficiency. Prior to the initiation of Depakote therapy, evaluation for UCD should be considered in the following patients: 1) those with a history of unexplained encephalopathy or coma, encephalopathy associated with a protein load, pregnancy-related or postpartum encephalopathy, unexplained mental retardation, or history of elevated plasma ammonia or glutamine; 2) those with cyclical vomiting and lethargy, episodic extreme irritability, ataxia, low BUN, or protein avoidance; 3) those with a family history of UCD or a family history of unexplained infant deaths (particularly males); 4) those with other signs or symptoms of UCD. Patients who develop symptoms of unexplained hyperammonemic encephalopathy while receiving valproate therapy should receive prompt treatment (including discontinuation of valproate therapy) and be evaluated for underlying urea cycle disorders [see Contraindications (4) and Warnings and Precautions (5.10)].

5.7 Suicidal Behavior and Ideation

Antiepileptic drugs (AEDs), including Depakote, increase the risk of suicidal thoughts or behavior in patients taking these drugs for any indication. Patients treated with any AED for any indication should be monitored for the emergence or worsening of depression, suicidal thoughts or behavior, and/or any unusual changes in mood or behavior.

Pooled analyses of 199 placebo-controlled clinical trials (mono- and adjunctive therapy) of 11 different AEDs showed that patients randomized to one of the AEDs had approximately twice the risk (adjusted Relative Risk 1.8, 95% CI:1.2, 2.7) of suicidal thinking or behavior compared to patients randomized to placebo. In these trials, which had a median treatment duration of 12 weeks, the estimated incidence rate of suicidal behavior or ideation among 27,863 AED-treated patients was 0.43%, compared to 0.24% among 16,029 placebo-treated patients, representing an increase of approximately one case of suicidal thinking or behavior for every 530 patients treated. There were four suicides in drug-treated patients in the trials and none in placebo-treated patients, but the number is too small to allow any conclusion about drug effect on suicide.

The increased risk of suicidal thoughts or behavior with AEDs was observed as early as one week after starting drug treatment with AEDs and persisted for the duration of treatment assessed. Because most trials included in the analysis did not extend beyond 24 weeks, the risk of suicidal thoughts or behavior beyond 24 weeks could not be assessed.

The risk of suicidal thoughts or behavior was generally consistent among drugs in the data analyzed. The finding of increased risk with AEDs of varying mechanisms of action and across a range of indications suggests that the risk applies to all AEDs used for any indication. The risk did not vary substantially by age (5-100 years) in the clinical trials analyzed.

Table 1 shows absolute and relative risk by indication for all evaluated AEDs.

Table 1. Risk by Indication for Antiepileptic Drugs in the Pooled Analysis
Indication | Placebo Patients with Events Per 1,000 Patients | Drug Patients with Events Per 1,000 Patients | Relative Risk: Incidence of Events in Drug Patients/Incidence in Placebo Patients | Risk Difference: Additional Drug Patients with Events Per 1,000 Patients
Epilepsy | 1.0 | 3.4 | 3.5 | 2.4
Psychiatric | 5.7 | 8.5 | 1.5 | 2.9
Other | 1.0 | 1.8 | 1.9 | 0.9
Total | 2.4 | 4.3 | 1.8 | 1.9

The relative risk for suicidal thoughts or behavior was higher in clinical trials for epilepsy than in clinical trials for psychiatric or other conditions, but the absolute risk differences were similar for the epilepsy and psychiatric indications.

Anyone considering prescribing Depakote or any other AED must balance the risk of suicidal thoughts or behavior with the risk of untreated illness. Epilepsy and many other illnesses for which AEDs are prescribed are themselves associated with morbidity and mortality and an increased risk of suicidal thoughts and behavior. Should suicidal thoughts and behavior emerge during treatment, the prescriber needs to consider whether the emergence of these symptoms in any given patient may be related to the illness being treated.

5.8 Bleeding and Other Hematopoietic Disorders

Valproate is associated with dose-related thrombocytopenia. In a clinical trial of valproate as monotherapy in patients with epilepsy, 34/126 patients (27%) receiving approximately 50 mg/kg/day on average, had at least one value of platelets ≤ 75 x 10^9/L. Approximately half of these patients had treatment discontinued, with return of platelet counts to normal. In the remaining patients, platelet counts normalized with continued treatment. In this study, the probability of thrombocytopenia appeared to increase significantly at total valproate concentrations of ≥ 110 mcg/mL (females) or ≥ 135 mcg/mL (males). The therapeutic benefit which may accompany the higher doses should therefore be weighed against the possibility of a greater incidence of adverse effects. Valproate use has also been associated with decreases in other cell lines and myelodysplasia.

Because of reports of cytopenias, inhibition of the secondary phase of platelet aggregation, and abnormal coagulation parameters, (e.g., low fibrinogen, coagulation factor deficiencies, acquired von Willebrand’s disease), measurements of complete blood counts and coagulation tests are recommended before initiating therapy and at periodic intervals. It is recommended that patients receiving Depakote be monitored for blood counts and coagulation parameters prior to planned surgery and during pregnancy [see Use in Specific Populations (8.1)]. Evidence of hemorrhage, bruising, or a disorder of hemostasis/coagulation is an indication for reduction of the dosage or withdrawal of therapy.

5.9 Hyperammonemia

Hyperammonemia has been reported in association with valproate therapy and may be present despite normal liver function tests. In patients who develop unexplained lethargy and vomiting or changes in mental status, hyperammonemic encephalopathy should be considered and an ammonia level should be measured. Hyperammonemia should also be considered in patients who present with hypothermia [see Warnings and Precautions (5.11)]. If ammonia is increased, valproate therapy should be discontinued. Appropriate interventions for treatment of hyperammonemia should be initiated, and such patients should undergo investigation for underlying urea cycle disorders [see Contraindications (4) and Warnings and Precautions (5.6, 5.10)].

Asymptomatic elevations of ammonia are more common and when present, require close monitoring of plasma ammonia levels. If the elevation persists, discontinuation of valproate therapy should be considered.

5.10 Hyperammonemia and Encephalopathy Associated with Concomitant Topiramate Use

Concomitant administration of topiramate and valproate has been associated with hyperammonemia with or without encephalopathy in patients who have tolerated either drug alone. Clinical symptoms of hyperammonemic encephalopathy often include acute alterations in level of consciousness and/or cognitive function with lethargy or vomiting. Hypothermia can also be a manifestation of hyperammonemia [see Warnings and Precautions (5.11)]. In most cases, symptoms and signs abated with discontinuation of either drug. This adverse reaction is not due to a pharmacokinetic interaction. Patients with inborn errors of metabolism or reduced hepatic mitochondrial activity may be at an increased risk for hyperammonemia with or without encephalopathy. Although not studied, an interaction of topiramate and valproate may exacerbate existing defects or unmask deficiencies in susceptible persons. In patients who develop unexplained lethargy, vomiting, or changes in mental status, hyperammonemic encephalopathy should be considered and an ammonia level should be measured [see Contraindications (4) and Warnings and Precautions (5.6, 5.9)].

5.11 Hypothermia

Hypothermia, defined as an unintentional drop in body core temperature to <35°C (95°F), has been reported in association with valproate therapy both in conjunction with and in the absence of hyperammonemia. This adverse reaction can also occur in patients using concomitant topiramate with valproate after starting topiramate treatment or after increasing the daily dose of topiramate [see Drug Interactions (7.3)]. Consideration should be given to stopping valproate in patients who develop hypothermia, which may be manifested by a variety of clinical abnormalities including lethargy, confusion, coma, and significant alterations in other major organ systems such as the cardiovascular and respiratory systems. Clinical management and assessment should include examination of blood ammonia levels.

5.12 Drug Reaction with Eosinophilia and Systemic Symptoms (DRESS)/Multiorgan Hypersensitivity Reactions

Drug Reaction with Eosinophilia and Systemic Symptoms (DRESS), also known as multiorgan hypersensitivity, has been reported in patients taking valproate. DRESS may be fatal or life-threatening. DRESS typically, although not exclusively, presents with fever, rash, lymphadenopathy, and/or facial swelling, in association with other organ system involvement, such as hepatitis, nephritis, hematological abnormalities, myocarditis, or myositis sometimes resembling an acute viral infection. Eosinophilia is often present. Because this disorder is variable in its expression, other organ systems not noted here may be involved. It is important to note that early manifestations of hypersensitivity, such as fever or lymphadenopathy, may be present even though rash is not evident. If such signs or symptoms are present, the patient should be evaluated immediately. Valproate should be discontinued if an alternative etiology for the signs or symptoms cannot be established.

5.13 Serious Dermatologic Reactions

Serious and sometimes fatal dermatologic reactions, including toxic epidermal necrolysis (TEN), Stevens Johnson syndrome (SJS), acute generalized exanthematous pustulosis (AGEP), and erythema multiforme (EM) have been reported with valproate treatment. Valproate should be discontinued at the first sign of a rash, unless the rash is clearly not drug related. If a rash occurs, the patient should be evaluated for signs and symptoms of Drug Reaction with Eosinophilia and Systemic Symptoms (DRESS) [see Warnings and Precautions (5.12)]. If signs or symptoms suggest TEN/SJS/AGEP/EM, use of this drug should not be resumed, and alternative therapy should be considered.

5.14 Angioedema

Angioedema has been reported in patients treated with valproate in the postmarketing setting. Valproate should be discontinued immediately if symptoms of angioedema such as facial, perioral, or upper airway swelling occur. Valproate should be discontinued permanently if a clear alternative etiology for the reaction cannot be established [see Contraindications (4)].

5.15 Interaction with Carbapenem Antibiotics

Carbapenem antibiotics (for example, ertapenem, imipenem, meropenem; this is not a complete list) may reduce serum valproate concentrations to subtherapeutic levels, resulting in loss of seizure control. Serum valproate concentrations should be monitored frequently after initiating carbapenem therapy. Alternative antibacterial or anticonvulsant therapy should be considered if serum valproate concentrations drop significantly or seizure control deteriorates [see Drug Interactions (7.1)].

5.16 Somnolence in the Elderly

In a double-blind, multicenter trial of valproate in elderly patients with dementia (mean age = 83 years), doses were increased by 125 mg/day to a target dose of 20 mg/kg/day. A significantly higher proportion of valproate patients had somnolence compared to placebo, and although not statistically significant, there was a higher proportion of patients with dehydration. Discontinuations for somnolence were also significantly higher than with placebo. In some patients with somnolence (approximately one-half), there was associated reduced nutritional intake and weight loss. There was a trend for the patients who experienced these events to have a lower baseline albumin concentration, lower valproate clearance, and a higher BUN. In elderly patients, dosage should be increased more slowly and with regular monitoring for fluid and nutritional intake, dehydration, somnolence, and other adverse reactions. Dose reductions or discontinuation of valproate should be considered in patients with decreased food or fluid intake and in patients with excessive somnolence [see Dosage and Administration (2.4)].

5.17 Monitoring: Drug Plasma Concentration

Since valproate may interact with concurrently administered drugs which are capable of enzyme induction, periodic plasma concentration determinations of valproate and concomitant drugs are recommended during the early course of therapy [see Drug Interactions (7)].

5.18 Effect on Ketone and Thyroid Function Tests

Valproate is partially eliminated in the urine as a keto-metabolite which may lead to a false interpretation of the urine ketone test.

There have been reports of altered thyroid function tests associated with valproate. The clinical significance of these is unknown.

5.19 Effect on HIV and CMV Viruses Replication

There are in vitro studies that suggest valproate stimulates the replication of the HIV and CMV viruses under certain experimental conditions. The clinical consequence, if any, is not known. Additionally, the relevance of these in vitro findings is uncertain for patients receiving maximally suppressive antiretroviral therapy. Nevertheless, these data should be borne in mind when interpreting the results from regular monitoring of the viral load in HIV infected patients receiving valproate or when following CMV infected patients clinically.

5.20 Medication Residue in the Stool

There have been rare reports of medication residue in the stool. Some patients have had anatomic (including ileostomy or colostomy) or functional gastrointestinal disorders with shortened GI transit times. In some reports, medication residues have occurred in the context of diarrhea. It is recommended that plasma valproate levels be checked in patients who experience medication residue in the stool, and patients’ clinical condition should be monitored. If clinically indicated, alternative treatment may be considered.

6 ADVERSE REACTIONS

The following serious adverse reactions are described below and elsewhere in the labeling:

- Hepatic Failure [see Warnings and Precautions (5.1)]
- Birth Defects [see Warnings and Precautions (5.2)]
- Decreased IQ Following in Utero Exposure [see Warnings and Precautions (5.3)]
- Pancreatitis [see Warnings and Precautions (5.5)]
- Hyperammonemic Encephalopathy [see Warnings and Precautions (5.6, 5.9, 5.10)]
- Suicidal Behavior and Ideation [see Warnings and Precautions (5.7)]
- Bleeding and Other Hematopoietic Disorders [see Warnings and Precautions (5.8)]
- Hypothermia [see Warnings and Precautions (5.11)]
- Drug Reaction with Eosinophilia and Systemic Symptoms (DRESS)/Multiorgan Hypersensitivity Reactions [see Warnings and Precautions (5.12)]
- Serious Dermatologic Reactions [see Warnings and Precautions (5.13)]
- Angioedema [see Warnings and Precautions (5.14)]
- Somnolence in the Elderly [see Warnings and Precautions (5.16)]

Because clinical studies are conducted under widely varying conditions, adverse reaction rates observed in the clinical studies of a drug cannot be directly compared to rates in the clinical studies of another drug and may not reflect the rates observed in practice.

6.1 Mania

The incidence of treatment-emergent events has been ascertained based on combined data from two three week placebo-controlled clinical trials of Depakote in the treatment of manic episodes associated with bipolar disorder. The adverse reactions were usually mild or moderate in intensity, but sometimes were serious enough to interrupt treatment. In clinical trials, the rates of premature termination due to intolerance were not statistically different between placebo, Depakote, and lithium carbonate. A total of 4%, 8% and 11% of patients discontinued therapy due to intolerance in the placebo, Depakote, and lithium carbonate groups, respectively.

Table 2 summarizes those adverse reactions reported for patients in these trials where the incidence rate in the Depakote-treated group was greater than 5% and greater than the placebo incidence, or where the incidence in the Depakote-treated group was statistically significantly greater than the placebo group. Vomiting was the only reaction that was reported by significantly (p ≤ 0.05) more patients receiving Depakote compared to placebo.

Table 2. Adverse Reactions Reported by > 5% of Depakote-Treated Patients During Placebo-Controlled Trials of Acute Mania^1
Adverse Reaction | Depakote (n = 89) % | Placebo (n = 97) %
Nausea | 22 | 15
Somnolence | 19 | 12
Dizziness | 12 | 4
Vomiting | 12 | 3
Accidental Injury | 11 | 5
Asthenia | 10 | 7
Abdominal Pain | 9 | 8
Dyspepsia | 9 | 8
Rash | 6 | 3
^1 The following adverse reactions occurred at an equal or greater incidence for placebo than for Depakote: back pain, headache, constipation, diarrhea, tremor, and pharyngitis.

The following additional adverse reactions were reported by greater than 1% but not more than 5% of the 89 Depakote-treated patients in controlled clinical trials:

Body as a Whole: Chest pain, chills, chills and fever, fever, neck pain, neck rigidity.

Cardiovascular System: Hypertension, hypotension, palpitations, postural hypotension, tachycardia, vasodilation.

Digestive System: Anorexia, fecal incontinence, flatulence, gastroenteritis, glossitis, periodontal abscess.

Hemic and Lymphatic System: Ecchymosis.

Metabolic and Nutritional Disorders: Edema, peripheral edema.

Musculoskeletal System: Arthralgia, arthrosis, leg cramps, twitching.

Nervous System: Abnormal dreams, abnormal gait, agitation, ataxia, catatonic reaction, confusion, depression, diplopia, dysarthria, hallucinations, hypertonia, hypokinesia, insomnia, paresthesia, reflexes increased, tardive dyskinesia, thinking abnormalities, vertigo.

Respiratory System: Dyspnea, rhinitis.

Skin and Appendages: Alopecia, discoid lupus erythematosus, dry skin, furunculosis, maculopapular rash, seborrhea.

Special Senses: Amblyopia, conjunctivitis, deafness, dry eyes, ear pain, eye pain, tinnitus.

Urogenital System: Dysmenorrhea, dysuria, urinary incontinence.

6.2 Epilepsy

Based on a placebo-controlled trial of adjunctive therapy for treatment of complex partial seizures, Depakote was generally well tolerated with most adverse reactions rated as mild to moderate in severity. Intolerance was the primary reason for discontinuation in the Depakote-treated patients (6%), compared to 1% of placebo-treated patients.

Table 3 lists treatment-emergent adverse reactions which were reported by ≥ 5% of Depakote-treated patients and for which the incidence was greater than in the placebo group, in the placebo-controlled trial of adjunctive therapy for treatment of complex partial seizures. Since patients were also treated with other antiepilepsy drugs, it is not possible, in most cases, to determine whether the following adverse reactions can be ascribed to Depakote alone, or the combination of Depakote and other antiepilepsy drugs.

Table 3. Adverse Reactions Reported by ≥ 5% of Patients Treated with Depakote During Placebo-Controlled Trial of Adjunctive Therapy for Complex Partial Seizures
Body System/Reaction | Depakote (n = 77) % | Placebo (n = 70) %
Body as a Whole
Headache | 31 | 21
Asthenia | 27 | 7
Fever | 6 | 4
Gastrointestinal System
Nausea | 48 | 14
Vomiting | 27 | 7
Abdominal Pain | 23 | 6
Diarrhea | 13 | 6
Anorexia | 12 | 0
Dyspepsia | 8 | 4
Constipation | 5 | 1
Nervous System
Somnolence | 27 | 11
Tremor | 25 | 6
Dizziness | 25 | 13
Diplopia | 16 | 9
Amblyopia/Blurred Vision | 12 | 9
Ataxia | 8 | 1
Nystagmus | 8 | 1
Emotional Lability | 6 | 4
Thinking Abnormal | 6 | 0
Amnesia | 5 | 1
Respiratory System
Flu Syndrome | 12 | 9
Infection | 12 | 6
Bronchitis | 5 | 1
Rhinitis | 5 | 4
Other
Alopecia | 6 | 1
Weight Loss | 6 | 0

Table 4 lists treatment-emergent adverse reactions which were reported by ≥ 5% of patients in the high dose valproate group, and for which the incidence was greater than in the low dose group, in a controlled trial of Depakote monotherapy treatment of complex partial seizures. Since patients were being titrated off another antiepilepsy drug during the first portion of the trial, it is not possible, in many cases, to determine whether the following adverse reactions can be ascribed to Depakote alone, or the combination of valproate and other antiepilepsy drugs.

Table 4. Adverse Reactions Reported by ≥ 5% of Patients in the High Dose Group in the Controlled Trial of Valproate Monotherapy for Complex Partial Seizures^1
Body System/Reaction | High Dose (n = 131) % | Low Dose (n = 134) %
Body as a Whole
Asthenia | 21 | 10
Digestive System
Nausea | 34 | 26
Diarrhea | 23 | 19
Vomiting | 23 | 15
Abdominal Pain | 12 | 9
Anorexia | 11 | 4
Dyspepsia | 11 | 10
Hemic/Lymphatic System
Thrombocytopenia | 24 | 1
Ecchymosis | 5 | 4
Metabolic/Nutritional
Weight Gain | 9 | 4
Peripheral Edema | 8 | 3
Nervous System
Tremor | 57 | 19
Somnolence | 30 | 18
Dizziness | 18 | 13
Insomnia | 15 | 9
Nervousness | 11 | 7
Amnesia | 7 | 4
Nystagmus | 7 | 1
Depression | 5 | 4
Respiratory System
Infection | 20 | 13
Pharyngitis | 8 | 2
Dyspnea | 5 | 1
Skin and Appendages
Alopecia | 24 | 13
Special Senses
Amblyopia/Blurred Vision | 8 | 4
Tinnitus | 7 | 1
^1 Headache was the only adverse reaction that occurred in ≥ 5% of patients in the high dose group and at an equal or greater incidence in the low dose group.

The following additional adverse reactions were reported by greater than 1% but less than 5% of the 358 patients treated with valproate in the controlled trials of complex partial seizures:

Body as a Whole: Back pain, chest pain, malaise.

Cardiovascular System: Tachycardia, hypertension, palpitation.

Digestive System: Increased appetite, flatulence, hematemesis, eructation, pancreatitis, periodontal abscess.

Hemic and Lymphatic System: Petechia.

Metabolic and Nutritional Disorders: SGOT increased, SGPT increased.

Musculoskeletal System: Myalgia, twitching, arthralgia, leg cramps, myasthenia.

Nervous System: Anxiety, confusion, abnormal gait, paresthesia, hypertonia, incoordination, abnormal dreams, personality disorder.

Respiratory System: Sinusitis, cough increased, pneumonia, epistaxis.

Skin and Appendages: Rash, pruritus, dry skin.

Special Senses: Taste perversion, abnormal vision, deafness, otitis media.

Urogenital System: Urinary incontinence, vaginitis, dysmenorrhea, amenorrhea, urinary frequency.

6.3 Migraine

Based on two placebo-controlled clinical trials and their long term extension, valproate was generally well tolerated with most adverse reactions rated as mild to moderate in severity. Of the 202 patients exposed to valproate in the placebo-controlled trials, 17% discontinued for intolerance. This is compared to a rate of 5% for the 81 placebo patients. Including the long term extension study, the adverse reactions reported as the primary reason for discontinuation by ≥ 1% of 248 valproate-treated patients were alopecia (6%), nausea and/or vomiting (5%), weight gain (2%), tremor (2%), somnolence (1%), elevated SGOT and/or SGPT (1%), and depression (1%).

Table 5 includes those adverse reactions reported for patients in the placebo-controlled trials where the incidence rate in the Depakote-treated group was greater than 5% and was greater than that for placebo patients.

Table 5. Adverse Reactions Reported by > 5% of Depakote-Treated Patients During Migraine Placebo-Controlled Trials with a Greater Incidence Than Patients Taking Placebo^1
Body System Reaction | Depakote (N = 202) % | Placebo (N = 81) %
Gastrointestinal System
Nausea | 31 | 10
Dyspepsia | 13 | 9
Diarrhea | 12 | 7
Vomiting | 11 | 1
Abdominal Pain | 9 | 4
Increased Appetite | 6 | 4
Nervous System
Asthenia | 20 | 9
Somnolence | 17 | 5
Dizziness | 12 | 6
Tremor | 9 | 0
Other
Weight Gain | 8 | 2
Back Pain | 8 | 6
Alopecia | 7 | 1
^1 The following adverse reactions occurred in at least 5% of Depakote-treated patients and at an equal or greater incidence for placebo than for Depakote: flu syndrome and pharyngitis.

The following additional adverse reactions were reported by greater than 1% but not more than 5% of the 202 Depakote-treated patients in the controlled clinical trials:

Body as a Whole: Chest pain, chills, face edema, fever and malaise.

Cardiovascular System: Vasodilatation.

Digestive System: Anorexia, constipation, dry mouth, flatulence, gastrointestinal disorder (unspecified), and stomatitis.

Hemic and Lymphatic System: Ecchymosis.

Metabolic and Nutritional Disorders: Peripheral edema, SGOT increase, and SGPT increase.

Musculoskeletal System: Leg cramps and myalgia.

Nervous System: Abnormal dreams, amnesia, confusion, depression, emotional lability, insomnia, nervousness, paresthesia, speech disorder, thinking abnormalities, and vertigo.

Respiratory System: Cough increased, dyspnea, rhinitis, and sinusitis.

Skin and Appendages: Pruritus and rash.

Special Senses: Conjunctivitis, ear disorder, taste perversion, and tinnitus.

Urogenital System: Cystitis, metrorrhagia, and vaginal hemorrhage.

6.4 Postmarketing Experience

The following adverse reactions have been identified during post approval use of Depakote. Because these reactions are reported voluntarily from a population of uncertain size, it is not always possible to reliably estimate their frequency or establish a causal relationship to drug exposure.

Dermatologic: Hair texture changes, hair color changes, photosensitivity, erythema multiforme, toxic epidermal necrolysis, nail and nail bed disorders, Stevens-Johnson syndrome, hyperpigmentation, and acute generalized exanthematous pustulosis [see Warnings and Precautions (5.13)].

Psychiatric: Emotional upset, psychosis, aggression, psychomotor hyperactivity, hostility, disturbance in attention, learning disorder, and behavioral deterioration.

Neurologic: Paradoxical convulsion, parkinsonism

There have been several reports of acute or subacute cognitive decline and behavioral changes (apathy or irritability) with cerebral pseudoatrophy on imaging associated with valproate therapy; both the cognitive/behavioral changes and cerebral pseudoatrophy reversed partially or fully after valproate discontinuation.

There have been reports of acute or subacute encephalopathy in the absence of elevated ammonia levels, elevated valproate levels, or neuroimaging changes. The encephalopathy reversed partially or fully after valproate discontinuation.

Musculoskeletal: Fractures, decreased bone mineral density, osteopenia, osteoporosis, and weakness.

Hematologic: Relative lymphocytosis, macrocytosis, leukopenia, acquired Pelger-Huet anomaly, anemia including macrocytic with or without folate deficiency, bone marrow suppression, pancytopenia, aplastic anemia, agranulocytosis, and acute intermittent porphyria.

Endocrine: Irregular menses, secondary amenorrhea, hyperandrogenism, hirsutism, elevated testosterone level, breast enlargement, galactorrhea, parotid gland swelling, polycystic ovary disease, decreased carnitine concentrations, hyponatremia, hyperglycinemia, and inappropriate ADH secretion.

There have been rare reports of Fanconi's syndrome occurring chiefly in children.

Metabolism and nutrition: Weight gain.

Reproductive: Aspermia, azoospermia, decreased sperm count, decreased spermatozoa motility, male infertility, and abnormal spermatozoa morphology.

Genitourinary: Enuresis, urinary tract infection, and tubulointerstitial nephritis.

Special Senses: Hearing loss.

Other: Allergic reaction, anaphylaxis, developmental delay, bone pain, bradycardia, cutaneous vasculitis, and angioedema [see Warnings and Precautions (5.14)].

7 DRUG INTERACTIONS

7.1 Effects of Co-Administered Drugs on Valproate Clearance

Drugs that affect the level of expression of hepatic enzymes, particularly those that elevate levels of glucuronosyltransferases (such as ritonavir), may increase the clearance of valproate. For example, phenytoin, carbamazepine, and phenobarbital (or primidone) can double the clearance of valproate. Thus, patients on monotherapy will generally have longer half-lives and higher concentrations than patients receiving polytherapy with antiepilepsy drugs.

In contrast, drugs that are inhibitors of cytochrome P450 isozymes, e.g., antidepressants, may be expected to have little effect on valproate clearance because cytochrome P450 microsomal mediated oxidation is a relatively minor secondary metabolic pathway compared to glucuronidation and beta-oxidation.

Because of these changes in valproate clearance, monitoring of valproate and concomitant drug concentrations should be increased whenever enzyme inducing drugs are introduced or withdrawn.

The following list provides information about the potential for an influence of several commonly prescribed medications on valproate pharmacokinetics. The list is not exhaustive nor could it be, since new interactions are continuously being reported.

Drugs for which a potentially important interaction has been observed

Aspirin

A study involving the co-administration of aspirin at antipyretic doses (11 to 16 mg/kg) with valproate to pediatric patients (n=6) revealed a decrease in protein binding and an inhibition of metabolism of valproate. Valproate free fraction was increased 4-fold in the presence of aspirin compared to valproate alone. The β-oxidation pathway consisting of 2-E-valproic acid, 3-OH-valproic acid, and 3-keto valproic acid was decreased from 25% of total metabolites excreted on valproate alone to 8.3% in the presence of aspirin. Caution should be observed if valproate and aspirin are to be co-administered.

Carbapenem Antibiotics

A clinically significant reduction in serum valproic acid concentration has been reported in patients receiving carbapenem antibiotics (for example, ertapenem, imipenem, meropenem; this is not a complete list) and may result in loss of seizure control. The mechanism of this interaction is not well understood. Serum valproic acid concentrations should be monitored frequently after initiating carbapenem therapy. Alternative antibacterial or anticonvulsant therapy should be considered if serum valproic acid concentrations drop significantly or seizure control deteriorates [see Warnings and Precautions (5.15)].

Estrogen-Containing Hormonal Contraceptives

Estrogen-containing hormonal contraceptives may increase the clearance of valproate, which may result in decreased concentration of valproate and potentially increased seizure frequency. Prescribers should monitor serum valproate concentrations and clinical response when adding or discontinuing estrogen containing products.

Felbamate

A study involving the co-administration of 1,200 mg/day of felbamate with valproate to patients with epilepsy (n=10) revealed an increase in mean valproate peak concentration by 35% (from 86 to 115 mcg/mL) compared to valproate alone. Increasing the felbamate dose to 2,400 mg/day increased the mean valproate peak concentration to 133 mcg/mL (another 16% increase). A decrease in valproate dosage may be necessary when felbamate therapy is initiated.

Methotrexate

Methotrexate may decrease serum valproate levels and potentially result in increased frequency of seizures or bipolar symptoms. Prescribers should monitor serum valproate concentrations and clinical response when adding or discontinuing methotrexate and adjust valproate dosage, if necessary.

Rifampin

A study involving the administration of a single dose of valproate (7 mg/kg) 36 hours after 5 nights of daily dosing with rifampin (600 mg) revealed a 40% increase in the oral clearance of valproate. Valproate dosage adjustment may be necessary when it is co-administered with rifampin.

7.2 Effects of Valproate on Other Drugs

Valproate has been found to be a weak inhibitor of some P450 isozymes, epoxide hydrase, and glucuronosyltransferases.

The following list provides information about the potential for an influence of valproate co-administration on the pharmacokinetics or pharmacodynamics of several commonly prescribed medications. The list is not exhaustive, since new interactions are continuously being reported.

Drugs for which a potentially important valproate interaction has been observed

Amitriptyline/Nortriptyline

Administration of a single oral 50 mg dose of amitriptyline to 15 normal volunteers (10 males and 5 females) who received valproate (500 mg BID) resulted in a 21% decrease in plasma clearance of amitriptyline and a 34% decrease in the net clearance of nortriptyline. Rare postmarketing reports of concurrent use of valproate and amitriptyline resulting in an increased amitriptyline level have been received. Concurrent use of valproate and amitriptyline has rarely been associated with toxicity. Monitoring of amitriptyline levels should be considered for patients taking valproate concomitantly with amitriptyline. Consideration should be given to lowering the dose of amitriptyline/nortriptyline in the presence of valproate.

Carbamazepine/carbamazepine-10,11-Epoxide

Serum levels of carbamazepine (CBZ) decreased 17% while that of carbamazepine-10,11-epoxide (CBZ-E) increased by 45% upon co-administration of valproate and CBZ to epileptic patients.

Clonazepam

The concomitant use of valproate and clonazepam may induce absence status in patients with a history of absence type seizures.

Diazepam

Valproate displaces diazepam from its plasma albumin binding sites and inhibits its metabolism. Co-administration of valproate (1,500 mg daily) increased the free fraction of diazepam (10 mg) by 90% in healthy volunteers (n=6). Plasma clearance and volume of distribution for free diazepam were reduced by 25% and 20%, respectively, in the presence of valproate. The elimination half-life of diazepam remained unchanged upon addition of valproate.

Ethosuximide

Valproate inhibits the metabolism of ethosuximide. Administration of a single ethosuximide dose of 500 mg with valproate (800 to 1,600 mg/day) to healthy volunteers (n=6) was accompanied by a 25% increase in elimination half-life of ethosuximide and a 15% decrease in its total clearance as compared to ethosuximide alone. Patients receiving valproate and ethosuximide, especially along with other anticonvulsants, should be monitored for alterations in serum concentrations of both drugs.

Lamotrigine

In a steady-state study involving 10 healthy volunteers, the elimination half-life of lamotrigine increased from 26 to 70 hours with valproate co-administration (a 165% increase). The dose of lamotrigine should be reduced when co-administered with valproate. Serious skin reactions (such as Stevens-Johnson syndrome and toxic epidermal necrolysis) have been reported with concomitant lamotrigine and valproate administration. See lamotrigine package insert for details on lamotrigine dosing with concomitant valproate administration.

Phenobarbital

Valproate was found to inhibit the metabolism of phenobarbital. Co-administration of valproate (250 mg BID for 14 days) with phenobarbital to normal subjects (n=6) resulted in a 50% increase in half-life and a 30% decrease in plasma clearance of phenobarbital (60 mg single-dose). The fraction of phenobarbital dose excreted unchanged increased by 50% in presence of valproate.

There is evidence for severe CNS depression, with or without significant elevations of barbiturate or valproate serum concentrations. All patients receiving concomitant barbiturate therapy should be closely monitored for neurological toxicity. Serum barbiturate concentrations should be obtained, if possible, and the barbiturate dosage decreased, if appropriate.

Primidone, which is metabolized to a barbiturate, may be involved in a similar interaction with valproate.

Phenytoin

Valproate displaces phenytoin from its plasma albumin binding sites and inhibits its hepatic metabolism. Co-administration of valproate (400 mg TID) with phenytoin (250 mg) in normal volunteers (n=7) was associated with a 60% increase in the free fraction of phenytoin. Total plasma clearance and apparent volume of distribution of phenytoin increased 30% in the presence of valproate. Both the clearance and apparent volume of distribution of free phenytoin were reduced by 25%.

In patients with epilepsy, there have been reports of breakthrough seizures occurring with the combination of valproate and phenytoin. The dosage of phenytoin should be adjusted as required by the clinical situation.

Propofol

The concomitant use of valproate and propofol may lead to increased blood levels of propofol. Reduce the dose of propofol when co-administering with valproate. Monitor patients closely for signs of increased sedation or cardiorespiratory depression.

Rufinamide

Based on a population pharmacokinetic analysis, rufinamide clearance was decreased by valproate. Rufinamide concentrations were increased by <16% to 70%, dependent on concentration of valproate (with the larger increases being seen in pediatric patients at high doses or concentrations of valproate). Patients stabilized on rufinamide before being prescribed valproate should begin valproate therapy at a low dose, and titrate to a clinically effective dose [see Dosage and Administration (2.5)]. Similarly, patients on valproate should begin at a rufinamide dose lower than 10 mg/kg per day (pediatric patients) or 400 mg per day (adults).

Tolbutamide

From in vitro experiments, the unbound fraction of tolbutamide was increased from 20% to 50% when added to plasma samples taken from patients treated with valproate. The clinical relevance of this displacement is unknown.

Warfarin

In an in vitro study, valproate increased the unbound fraction of warfarin by up to 32.6%. The therapeutic relevance of this is unknown; however, coagulation tests should be monitored if valproate therapy is instituted in patients taking anticoagulants.

Zidovudine

In six patients who were seropositive for HIV, the clearance of zidovudine (100 mg q8h) was decreased by 38% after administration of valproate (250 or 500 mg q8h); the half-life of zidovudine was unaffected.

7.3 Topiramate

Concomitant administration of valproate and topiramate has been associated with hyperammonemia with and without encephalopathy [see Contraindications (4) and Warnings and Precautions (5.6, 5.9, 5.10)]. Concomitant administration of topiramate with valproate has also been associated with hypothermia in patients who have tolerated either drug alone. It may be prudent to examine blood ammonia levels in patients in whom the onset of hypothermia has been reported [see Warnings and Precautions (5.9, 5.11)].

7.4 Cannabidiol

Concomitant administration of valproate and cannabidiol has been associated with an increased risk of ALT and/or AST elevation. This has been manageable by dose reduction or, in more severe cases, by discontinuation of one or both drugs. Liver function, including serum transaminase and total bilirubin levels, should be monitored during concomitant treatment [see Warnings and Precautions (5.1)].

8 USE IN SPECIFIC POPULATIONS

8.1 Pregnancy

Pregnancy Exposure Registry

There is a pregnancy exposure registry that monitors pregnancy outcomes in women exposed to antiepileptic drugs (AEDs), including Depakote, during pregnancy. Encourage women who are taking Depakote during pregnancy to enroll in the North American Antiepileptic Drug (NAAED) Pregnancy Registry by calling toll-free 1-888-233-2334 or visiting the website, http://www.aedpregnancyregistry.org/. This must be done by the patient herself.

Risk Summary

For use in prophylaxis of migraine headaches, valproate is contraindicated in women who are pregnant and in women of childbearing potential who are not using effective contraception [see Contraindications (4)].

For use in epilepsy or bipolar disorder, valproate should not be used to treat women who are pregnant or who plan to become pregnant unless other medications have failed to provide adequate symptom control or are otherwise unacceptable [see Boxed Warning and Warnings and Precautions (5.2, 5.3)]. Women with epilepsy who become pregnant while taking valproate should not discontinue valproate abruptly, as this can precipitate status epilepticus with resulting maternal and fetal hypoxia and threat to life.

Maternal valproate use during pregnancy for any indication increases the risk of congenital malformations, particularly neural tube defects including spina bifida, but also malformations involving other body systems (e.g., craniofacial defects including oral clefts, cardiovascular malformations, hypospadias, limb malformations). This risk is dose-dependent; however, a threshold dose below which no risk exists cannot be established. In utero exposure to valproate may also result in hearing impairment or hearing loss. Valproate polytherapy with other AEDs has been associated with an increased frequency of congenital malformations compared with AED monotherapy. The risk of major structural abnormalities is greatest during the first trimester; however, other serious developmental effects can occur with valproate use throughout pregnancy. The rate of congenital malformations among babies born to epileptic mothers who used valproate during pregnancy has been shown to be about four times higher than the rate among babies born to epileptic mothers who used other anti-seizure monotherapies [see Warnings and Precautions (5.2) and Data (Human)].

Epidemiological studies have indicated that children exposed to valproate in utero have lower IQ scores and a higher risk of neurodevelopmental disorders compared to children exposed to either another AED in utero or to no AEDs in utero [see Warnings and Precautions (5.3) and Data (Human)].

An observational study has suggested that exposure to valproate products during pregnancy increases the risk of autism spectrum disorders [see Data (Human)].

In animal studies, valproate administration during pregnancy resulted in fetal structural malformations similar to those seen in humans and neurobehavioral deficits in the offspring at clinically relevant doses [see Data (Animal)].

There have been reports of hypoglycemia in neonates and fatal cases of hepatic failure in infants following maternal use of valproate during pregnancy.

Pregnant women taking valproate may develop hepatic failure or clotting abnormalities including thrombocytopenia, hypofibrinogenemia, and/or decrease in other coagulation factors, which may result in hemorrhagic complications in the neonate including death [see Warnings and Precautions (5.1, 5.8)].

Available prenatal diagnostic testing to detect neural tube and other defects should be offered to pregnant women using valproate.

Evidence suggests that folic acid supplementation prior to conception and during the first trimester of pregnancy decreases the risk for congenital neural tube defects in the general population. It is not known whether the risk of neural tube defects or decreased IQ in the offspring of women receiving valproate is reduced by folic acid supplementation. Dietary folic acid supplementation both prior to conception and during pregnancy should be routinely recommended for patients using valproate [see Warnings and Precautions (5.2, 5.4)].

All pregnancies have a background risk of birth defect, loss, or other adverse outcomes. In the U.S. general population, the estimated background risk of major birth defects and miscarriage in clinically recognized pregnancies is 2 to 4% and 15 to 20%, respectively.

Clinical Considerations

Disease-associated maternal and/or embryo/fetal risk

To prevent major seizures, women with epilepsy should not discontinue valproate abruptly, as this can precipitate status epilepticus with resulting maternal and fetal hypoxia and threat to life. Even minor seizures may pose some hazard to the developing embryo or fetus [see Warnings and Precautions (5.4)]. However, discontinuation of the drug may be considered prior to and during pregnancy in individual cases if the seizure disorder severity and frequency do not pose a serious threat to the patient.

Maternal adverse reactions

Pregnant women taking valproate may develop clotting abnormalities including thrombocytopenia, hypofibrinogenemia, and/or decrease in other coagulation factors, which may result in hemorrhagic complications in the neonate including death [see Warnings and Precautions (5.8)]. If valproate is used in pregnancy, the clotting parameters should be monitored carefully in the mother. If abnormal in the mother, then these parameters should also be monitored in the neonate.

Patients taking valproate may develop hepatic failure [see Boxed Warning and Warnings and Precautions (5.1)]. Fatal cases of hepatic failure in infants exposed to valproate in utero have also been reported following maternal use of valproate during pregnancy.

Hypoglycemia has been reported in neonates whose mothers have taken valproate during pregnancy.

Data

Human

Neural tube defects and other structural abnormalities

There is an extensive body of evidence demonstrating that exposure to valproate in utero increases the risk of neural tube defects and other structural abnormalities. Based on published data from the CDC’s National Birth Defects Prevention Network, the risk of spina bifida in the general population is about 0.06 to 0.07% (6 to 7 in 10,000 births) compared to the risk following in utero valproate exposure estimated to be approximately 1 to 2% (100 to 200 in 10,000 births).

The NAAED Pregnancy Registry has reported a major malformation rate of 9-11% in the offspring of women exposed to an average of 1,000 mg/day of valproate monotherapy during pregnancy. These data show an up to a five-fold increased risk for any major malformation following valproate exposure in utero compared to the risk following exposure in utero to other AEDs taken as monotherapy. The major congenital malformations included cases of neural tube defects, cardiovascular malformations, craniofacial defects (e.g., oral clefts, craniosynostosis), hypospadias, limb malformations (e.g., clubfoot, polydactyly), and other malformations of varying severity involving other body systems [see Warnings and Precautions (5.2)].

Effect on IQ and neurodevelopmental effects

Published epidemiological studies have indicated that children exposed to valproate in utero have lower IQ scores than children exposed to either another AED in utero or to no AEDs in utero. The largest of these studies^1 is a prospective cohort study conducted in the United States and United Kingdom that found that children with prenatal exposure to valproate (n=62) had lower IQ scores at age 6 (97 [95% C.I. 94-101]) than children with prenatal exposure to the other anti-epileptic drug monotherapy treatments evaluated: lamotrigine (108 [95% C.I. 105–110]), carbamazepine (105 [95% C.I. 102–108]) and phenytoin (108 [95% C.I. 104–112]). It is not known when during pregnancy cognitive effects in valproate-exposed children occur. Because the women in this study were exposed to AEDs throughout pregnancy, whether the risk for decreased IQ was related to a particular time period during pregnancy could not be assessed [see Warnings and Precautions (5.3)].

Although the available studies have methodological limitations, the weight of the evidence supports a causal association between valproate exposure in utero and subsequent adverse effects on neurodevelopment, including increases in autism spectrum disorders and attention deficit/hyperactivity disorder (ADHD). An observational study has suggested that exposure to valproate products during pregnancy increases the risk of autism spectrum disorders. In this study, children born to mothers who had used valproate products during pregnancy had 2.9 times the risk (95% confidence interval [CI]: 1.7-4.9) of developing autism spectrum disorders compared to children born to mothers not exposed to valproate products during pregnancy. The absolute risks for autism spectrum disorders were 4.4% (95% CI: 2.6%-7.5%) in valproate-exposed children and 1.5% (95% CI: 1.5%-1.6%) in children not exposed to valproate products. Another observational study found that children who were exposed to valproate in utero had an increased risk of ADHD (adjusted HR 1.48; 95% CI, 1.09-2.00) compared with the unexposed children. Because these studies were observational in nature, conclusions regarding a causal association between in utero valproate exposure and an increased risk of autism spectrum disorder and ADHD cannot be considered definitive.

Other

There are published case reports of fatal hepatic failure in offspring of women who used valproate during pregnancy.

Animal

In developmental toxicity studies conducted in mice, rats, rabbits, and monkeys, increased rates of fetal structural abnormalities, intrauterine growth retardation, and embryo-fetal death occurred following administration of valproate to pregnant animals during organogenesis at clinically relevant doses (calculated on a body surface area [mg/m^2] basis). Valproate induced malformations of multiple organ systems, including skeletal, cardiac, and urogenital defects. In mice, in addition to other malformations, fetal neural tube defects have been reported following valproate administration during critical periods of organogenesis, and the teratogenic response correlated with peak maternal drug levels. Behavioral abnormalities (including cognitive, locomotor, and social interaction deficits) and brain histopathological changes have also been reported in mice and rat offspring exposed prenatally to clinically relevant doses of valproate.

8.2 Lactation

Risk Summary

Valproate is excreted in human milk. Data in the published literature describe the presence of valproate in human milk (range: 0.4 mcg/mL to 3.9 mcg/mL), corresponding to 1% to 10% of maternal serum levels. Valproate serum concentrations collected from breastfed infants aged 3 days postnatal to 12 weeks following delivery ranged from 0.7 mcg/mL to 4 mcg/mL, which were 1% to 6% of maternal serum valproate levels. A published study in children up to six years of age did not report adverse developmental or cognitive effects following exposure to valproate via breast milk [see Data (Human)].

There are no data to assess the effects of Depakote on milk production or excretion.

Clinical Considerations

The developmental and health benefits of breastfeeding should be considered along with the mother’s clinical need for Depakote and any potential adverse effects on the breastfed infant from Depakote or from the underlying maternal condition.

Monitor the breastfed infant for signs of liver damage including jaundice and unusual bruising or bleeding. There have been reports of hepatic failure and clotting abnormalities in offspring of women who used valproate during pregnancy [see Use in Specific Populations (8.1)].

Data

Human

In a published study, breast milk and maternal blood samples were obtained from 11 epilepsy patients taking valproate at doses ranging from 300 mg/day to 2,400 mg/day on postnatal days 3 to 6. In 4 patients who were taking valproate only, breast milk contained an average valproate concentration of 1.8 mcg/mL (range: 1.1 mcg/mL to 2.2 mcg/mL), which corresponded to 4.8% of the maternal plasma concentration (range: 2.7% to 7.4%). Across all patients (7 of whom were taking other AEDs concomitantly), similar results were obtained for breast milk concentration (1.8 mcg/mL, range: 0.4 mcg/mL to 3.9 mcg/mL) and maternal plasma ratio (5.1%, range: 1.3% to 9.6%).

A published study of 6 breastfeeding mother-infant pairs measured serum valproate levels during maternal treatment for bipolar disorder (750 mg/day or 1,000 mg/day). None of the mothers received valproate during pregnancy, and infants were aged from 4 weeks to 19 weeks at the time of evaluation. Infant serum levels ranged from 0.7 mcg/mL to 1.5 mcg/mL. With maternal serum valproate levels near or within the therapeutic range, infant exposure was 0.9% to 2.3% of maternal levels. Similarly, in 2 published case reports with maternal doses of 500 mg/day or 750 mg/day during breastfeeding of infants aged 3 months and 1 month, infant exposure was 1.5% and 6% that of the mother, respectively.

A prospective observational multicenter study evaluated the long-term neurodevelopmental effects of AED use on children. Pregnant women receiving monotherapy for epilepsy were enrolled with assessments of their children at ages 3 years and 6 years. Mothers continued AED therapy during the breastfeeding period. Adjusted IQs measured at 3 years for breastfed and non-breastfed children were 93 (n=11) and 90 (n=24), respectively. At 6 years, the scores for breastfed and non-breastfed children were 106 (n=11) and 94 (n=25), respectively (p=0.04). For other cognitive domains evaluated at 6 years, no adverse cognitive effects of continued exposure to an AED (including valproate) via breast milk were observed.

8.3 Females and Males of Reproductive Potential

Contraception

Women of childbearing potential should use effective contraception while taking valproate [see Boxed Warning, Warnings and Precautions (5.4), Drug Interactions (7), and Use in Specific Populations (8.1)]. This is especially important when valproate use is considered for a condition not usually associated with permanent injury or death such as prophylaxis of migraine headaches [see Contraindications (4)].

Infertility

There have been reports of male infertility coincident with valproate therapy [see Adverse Reactions (6.4)].

In animal studies, oral administration of valproate at clinically relevant doses resulted in adverse reproductive effects in males [see Nonclinical Toxicology (13.1)].

8.4 Pediatric Use

Experience has indicated that pediatric patients under the age of two years are at a considerably increased risk of developing fatal hepatotoxicity, especially those with the aforementioned conditions [see Boxed Warning and Warnings and Precautions (5.1)]. When Depakote is used in this patient group, it should be used with extreme caution and as a sole agent. The benefits of therapy should be weighed against the risks. Above the age of 2 years, experience in epilepsy has indicated that the incidence of fatal hepatotoxicity decreases considerably in progressively older patient groups.

Younger children, especially those receiving enzyme-inducing drugs, will require larger maintenance doses to attain targeted total and unbound valproate concentrations. Pediatric patients (i.e., between 3 months and 10 years) have 50% higher clearances expressed on weight (i.e., mL/min/kg) than do adults. Over the age of 10 years, children have pharmacokinetic parameters that approximate those of adults.

The variability in free fraction limits the clinical usefulness of monitoring total serum valproic acid concentrations. Interpretation of valproic acid concentrations in children should include consideration of factors that affect hepatic metabolism and protein binding.

Pediatric Clinical Trials

Depakote was studied in seven pediatric clinical trials.

Two of the pediatric studies were double-blinded placebo-controlled trials to evaluate the efficacy of Depakote ER for the indications of mania (150 patients aged 10 to 17 years, 76 of whom were on Depakote ER) and migraine (304 patients aged 12 to 17 years, 231 of whom were on Depakote ER). Efficacy was not established for either the treatment of migraine or the treatment of mania. The most common drug-related adverse reactions (reported >5% and twice the rate of placebo) reported in the controlled pediatric mania study were nausea, upper abdominal pain, somnolence, increased ammonia, gastritis and rash.

The remaining five trials were long term safety studies. Two six-month pediatric studies were conducted to evaluate the long-term safety of Depakote ER for the indication of mania (292 patients aged 10 to 17 years). Two twelve-month pediatric studies were conducted to evaluate the long-term safety of Depakote ER for the indication of migraine (353 patients aged 12 to 17 years). One twelve-month study was conducted to evaluate the safety of Depakote Sprinkle Capsules in the indication of partial seizures (169 patients aged 3 to 10 years).

In these seven clinical trials, the safety and tolerability of Depakote in pediatric patients were shown to be comparable to those in adults [see Adverse Reactions (6)].

Juvenile Animal Toxicology

In studies of valproate in immature animals, toxic effects not observed in adult animals included retinal dysplasia in rats treated during the neonatal period (from postnatal day 4) and nephrotoxicity in rats treated during the neonatal and juvenile (from postnatal day 14) periods. The no-effect dose for these findings was less than the maximum recommended human dose on a mg/m^2 basis.

8.5 Geriatric Use

No patients above the age of 65 years were enrolled in double-blind prospective clinical trials of mania associated with bipolar illness. In a case review study of 583 patients, 72 patients (12%) were greater than 65 years of age. A higher percentage of patients above 65 years of age reported accidental injury, infection, pain, somnolence, and tremor. Discontinuation of valproate was occasionally associated with the latter two events. It is not clear whether these events indicate additional risk or whether they result from preexisting medical illness and concomitant medication use among these patients.

A study of elderly patients with dementia revealed drug related somnolence and discontinuation for somnolence [see Warnings and Precautions (5.16)]. The starting dose should be reduced in these patients, and dosage reductions or discontinuation should be considered in patients with excessive somnolence [see Dosage and Administration (2.4)].

There is insufficient information available to discern the safety and effectiveness of valproate for the prophylaxis of migraines in patients over 65.

10 OVERDOSAGE

Overdosage with valproate may result in somnolence, heart block, deep coma, and hypernatremia. Fatalities have been reported; however patients have recovered from valproate levels as high as 2,120 mcg/mL.

In overdose situations, the fraction of drug not bound to protein is high and hemodialysis or tandem hemodialysis plus hemoperfusion may result in significant removal of drug. The benefit of gastric lavage or emesis will vary with the time since ingestion. General supportive measures should be applied with particular attention to the maintenance of adequate urinary output.

Naloxone has been reported to reverse the CNS depressant effects of valproate overdosage. Because naloxone could theoretically also reverse the antiepileptic effects of valproate, it should be used with caution in patients with epilepsy.

11 DESCRIPTION

Divalproex sodium is a stable co-ordination compound comprised of sodium valproate and valproic acid in a 1:1 molar relationship and formed during the partial neutralization of valproic acid with 0.5 equivalent of sodium hydroxide. Chemically it is designated as sodium hydrogen bis(2-propylpentanoate). Divalproex sodium has the following structure:

Divalproex sodium occurs as a white powder with a characteristic odor.

Depakote tablets are for oral administration. Depakote tablets are supplied in three dosage strengths containing divalproex sodium equivalent to 125 mg, 250 mg, or 500 mg of valproic acid.

Inactive Ingredients

Depakote tablets: cellulosic polymers, diacetylated monoglycerides, povidone, pregelatinized starch (contains corn starch), silica gel, talc, titanium dioxide, and vanillin.

In addition, individual tablets contain:

125 mg tablets: FD&C Blue No. 1 and FD&C Red No. 40.

250 mg tablets: FD&C Yellow No. 6 and iron oxide.

500 mg tablets: D&C Red No. 30, FD&C Blue No. 2, and iron oxide.

12 CLINICAL PHARMACOLOGY

12.1 Mechanism of Action

Divalproex sodium dissociates to the valproate ion in the gastrointestinal tract. The mechanisms by which valproate exerts its therapeutic effects have not been established. It has been suggested that its activity in epilepsy is related to increased brain concentrations of gamma-aminobutyric acid (GABA).

12.2 Pharmacodynamics

The relationship between plasma concentration and clinical response is not well documented. One contributing factor is the nonlinear, concentration dependent protein binding of valproate which affects the clearance of the drug. Thus, monitoring of total serum valproate cannot provide a reliable index of the bioactive valproate species.

For example, because the plasma protein binding of valproate is concentration dependent, the free fraction increases from approximately 10% at 40 mcg/mL to 18.5% at 130 mcg/mL. Higher than expected free fractions occur in the elderly, in hyperlipidemic patients, and in patients with hepatic and renal diseases.

Epilepsy

The therapeutic range in epilepsy is commonly considered to be 50 to 100 mcg/mL of total valproate, although some patients may be controlled with lower or higher plasma concentrations.

Mania

In placebo-controlled clinical trials of acute mania, patients were dosed to clinical response with trough plasma concentrations between 50 and 125 mcg/mL [see Dosage and Administration (2.1)].

12.3 Pharmacokinetics

Absorption/Bioavailability

Equivalent oral doses of Depakote (divalproex sodium) products and valproic acid capsules deliver equivalent quantities of valproate ion systemically. Although the rate of valproate ion absorption may vary with the formulation administered (liquid, solid, or sprinkle), conditions of use (e.g., fasting or postprandial) and the method of administration (e.g., whether the contents of the capsule are sprinkled on food or the capsule is taken intact), these differences should be of minor clinical importance under the steady state conditions achieved in chronic use in the treatment of epilepsy.

However, it is possible that differences among the various valproate products in Tmax and Cmax could be important upon initiation of treatment. For example, in single dose studies, the effect of feeding had a greater influence on the rate of absorption of the tablet (increase in Tmax from 4 to 8 hours) than on the absorption of the sprinkle capsules (increase in Tmax from 3.3 to 4.8 hours).

While the absorption rate from the G.I. tract and fluctuation in valproate plasma concentrations vary with dosing regimen and formulation, the efficacy of valproate as an anticonvulsant in chronic use is unlikely to be affected. Experience employing dosing regimens from once-a-day to four-times-a-day, as well as studies in primate epilepsy models involving constant rate infusion, indicate that total daily systemic bioavailability (extent of absorption) is the primary determinant of seizure control and that differences in the ratios of plasma peak to trough concentrations between valproate formulations are inconsequential from a practical clinical standpoint. Whether or not rate of absorption influences the efficacy of valproate as an antimanic or antimigraine agent is unknown.

Co-administration of oral valproate products with food and substitution among the various Depakote and valproic acid formulations should cause no clinical problems in the management of patients with epilepsy [see Dosage and Administration (2.2)]. Nonetheless, any changes in dosage administration, or the addition or discontinuance of concomitant drugs should ordinarily be accompanied by close monitoring of clinical status and valproate plasma concentrations.

Distribution

Protein Binding

The plasma protein binding of valproate is concentration dependent and the free fraction increases from approximately 10% at 40 mcg/mL to 18.5% at 130 mcg/mL. Protein binding of valproate is reduced in the elderly, in patients with chronic hepatic diseases, in patients with renal impairment, and in the presence of other drugs (e.g., aspirin). Conversely, valproate may displace certain protein-bound drugs (e.g., phenytoin, carbamazepine, warfarin, and tolbutamide) [see Drug Interactions (7.2) for more detailed information on the pharmacokinetic interactions of valproate with other drugs].

CNS Distribution

Valproate concentrations in cerebrospinal fluid (CSF) approximate unbound concentrations in plasma (about 10% of total concentration).

Metabolism

Valproate is metabolized almost entirely by the liver. In adult patients on monotherapy, 30-50% of an administered dose appears in urine as a glucuronide conjugate. Mitochondrial β-oxidation is the other major metabolic pathway, typically accounting for over 40% of the dose. Usually, less than 15-20% of the dose is eliminated by other oxidative mechanisms. Less than 3% of an administered dose is excreted unchanged in urine.

The relationship between dose and total valproate concentration is nonlinear; concentration does not increase proportionally with the dose, but rather, increases to a lesser extent due to saturable plasma protein binding. The kinetics of unbound drug are linear.

Elimination

Mean plasma clearance and volume of distribution for total valproate are 0.56 L/hr/1.73 m^2 and 11 L/1.73 m^2, respectively. Mean plasma clearance and volume of distribution for free valproate are 4.6 L/hr/1.73 m^2 and 92 L/1.73 m^2. Mean terminal half-life for valproate monotherapy ranged from 9 to 16 hours following oral dosing regimens of 250 to 1,000 mg.

The estimates cited apply primarily to patients who are not taking drugs that affect hepatic metabolizing enzyme systems. For example, patients taking enzyme-inducing antiepileptic drugs (carbamazepine, phenytoin, and phenobarbital) will clear valproate more rapidly. Because of these changes in valproate clearance, monitoring of antiepileptic concentrations should be intensified whenever concomitant antiepileptics are introduced or withdrawn.

Specific Populations

Effect of Age

Neonates

Children within the first two months of life have a markedly decreased ability to eliminate valproate compared to older children and adults. This is a result of reduced clearance (perhaps due to delay in development of glucuronosyltransferase and other enzyme systems involved in valproate elimination) as well as increased volume of distribution (in part due to decreased plasma protein binding). For example, in one study, the half-life in children under 10 days ranged from 10 to 67 hours compared to a range of 7 to 13 hours in children greater than 2 months.

Children

Pediatric patients (i.e., between 3 months and 10 years) have 50% higher clearances expressed on weight (i.e., mL/min/kg) than do adults. Over the age of 10 years, children have pharmacokinetic parameters that approximate those of adults.

Elderly

The capacity of elderly patients (age range: 68 to 89 years) to eliminate valproate has been shown to be reduced compared to younger adults (age range: 22 to 26 years). Intrinsic clearance is reduced by 39%; the free fraction is increased by 44%. Accordingly, the initial dosage should be reduced in the elderly [see Dosage and Administration (2.4)].

Effect of Sex

There are no differences in the body surface area adjusted unbound clearance between males and females (4.8±0.17 and 4.7±0.07 L/hr per 1.73 m^2, respectively).

Effect of Race

The effects of race on the kinetics of valproate have not been studied.

Effect of Disease

Liver Disease

Liver disease impairs the capacity to eliminate valproate. In one study, the clearance of free valproate was decreased by 50% in 7 patients with cirrhosis and by 16% in 4 patients with acute hepatitis, compared with 6 healthy subjects. In that study, the half-life of valproate was increased from 12 to 18 hours. Liver disease is also associated with decreased albumin concentrations and larger unbound fractions (2 to 2.6 fold increase) of valproate. Accordingly, monitoring of total concentrations may be misleading since free concentrations may be substantially elevated in patients with hepatic disease whereas total concentrations may appear to be normal [see Boxed Warning, Contraindications (4), and Warnings and Precautions (5.1)].

Renal Disease

A slight reduction (27%) in the unbound clearance of valproate has been reported in patients with renal failure (creatinine clearance < 10 mL/minute); however, hemodialysis typically reduces valproate concentrations by about 20%. Therefore, no dosage adjustment appears to be necessary in patients with renal failure. Protein binding in these patients is substantially reduced; thus, monitoring total concentrations may be misleading.

Drug Interaction Studies with No Interaction or Likely Clinically Unimportant Interaction

Antacids

A study involving the co-administration of valproate 500 mg with commonly administered antacids (Maalox, Trisogel, and Titralac - 160 mEq doses) did not reveal any effect on the extent of absorption of valproate.

Chlorpromazine

A study involving the administration of 100 to 300 mg/day of chlorpromazine to schizophrenic patients already receiving valproate (200 mg BID) revealed a 15% increase in trough plasma levels of valproate.

Haloperidol

A study involving the administration of 6 to 10 mg/day of haloperidol to schizophrenic patients already receiving valproate (200 mg BID) revealed no significant changes in valproate trough plasma levels.

Cimetidine and Ranitidine

Cimetidine and ranitidine do not affect the clearance of valproate.

Acetaminophen

Valproate had no effect on any of the pharmacokinetic parameters of acetaminophen when it was concurrently administered to three epileptic patients.

Clozapine

In psychotic patients (n=11), no interaction was observed when valproate was co-administered with clozapine.

Lithium

Co-administration of valproate (500 mg BID) and lithium carbonate (300 mg TID) to normal male volunteers (n=16) had no effect on the steady-state kinetics of lithium.

Lorazepam

Concomitant administration of valproate (500 mg BID) and lorazepam (1 mg BID) in normal male volunteers (n=9) was accompanied by a 17% decrease in the plasma clearance of lorazepam.

Olanzapine

No dose adjustment for olanzapine is necessary when olanzapine is administered concomitantly with valproate. Co-administration of valproate (500 mg BID) and olanzapine (5 mg) to healthy adults (n=10) caused 15% reduction in Cmax and 35% reduction in AUC of olanzapine.

Oral Contraceptive Steroids

Administration of a single-dose of ethinyloestradiol (50 mcg)/levonorgestrel (250 mcg) to 6 women on valproate (200 mg BID) therapy for 2 months did not reveal any pharmacokinetic interaction.

13 NONCLINICAL TOXICOLOGY

13.1 Carcinogenesis, Mutagenesis, and Impairment of Fertility

Carcinogenesis

Valproate was administered orally to rats and mice at doses of 80 and 170 mg/kg/day (less than the maximum recommended human dose on a mg/m^2 basis) for two years. The primary findings were an increase in the incidence of subcutaneous fibrosarcomas in high-dose male rats receiving valproate and a dose-related trend for benign pulmonary adenomas in male mice receiving valproate.

Mutagenesis

Valproate was not mutagenic in an in vitro bacterial assay (Ames test), did not produce dominant lethal effects in mice, and did not increase chromosome aberration frequency in an in vivo cytogenetic study in rats. Increased frequencies of sister chromatid exchange (SCE) have been reported in a study of epileptic children taking valproate; this association was not observed in another study conducted in adults.

Impairment of Fertility

In chronic toxicity studies in juvenile and adult rats and dogs, administration of valproate resulted in testicular atrophy and reduced spermatogenesis at oral doses of 400 mg/kg/day or greater in rats (approximately equal to or greater than the maximum recommended human dose (MRHD) on a mg/m^2 basis) and 150 mg/kg/day or greater in dogs (approximately equal to or greater than the MRHD on a mg/m^2 basis). Fertility studies in rats have shown no effect on fertility at oral doses of valproate up to 350 mg/kg/day (approximately equal to the MRHD on a mg/m^2 basis) for 60 days.

14 CLINICAL STUDIES

14.1 Mania

The effectiveness of Depakote for the treatment of acute mania was demonstrated in two 3-week, placebo controlled, parallel group studies.

(1) Study 1: The first study enrolled adult patients who met DSM-III-R criteria for bipolar disorder and who were hospitalized for acute mania. In addition, they had a history of failing to respond to or not tolerating previous lithium carbonate treatment. Depakote was initiated at a dose of 250 mg tid and adjusted to achieve serum valproate concentrations in a range of 50-100 mcg/mL by day 7. Mean Depakote doses for completers in this study were 1,118, 1,525, and 2,402 mg/day at Days 7, 14, and 21, respectively. Patients were assessed on the Young Mania Rating Scale (YMRS; score ranges from 0-60), an augmented Brief Psychiatric Rating Scale (BPRS-A), and the Global Assessment Scale (GAS). Baseline scores and change from baseline in the Week 3 endpoint (last-observation-carry-forward) analysis were as follows:

Table 6. Study 1
YMRS Total Score
Group | Baseline^1 | BL to Wk 3^2 | Difference^3
Placebo | 28.8 | + 0.2
Depakote | 28.5 | - 9.5 | 9.7
BPRS-A Total Score
Group | Baseline^1 | BL to Wk 3^2 | Difference^3
Placebo | 76.2 | + 1.8
Depakote | 76.4 | -17.0 | 18.8
GAS Score
Group | Baseline^1 | BL to Wk 3^2 | Difference^3
Placebo | 31.8 | 0.0
Depakote | 30.3 | + 18.1 | 18.1
^1 Mean score at baseline
^2 Change from baseline to Week 3 (LOCF)
^3 Difference in change from baseline to Week 3 endpoint (LOCF) between Depakote and placebo

Depakote was statistically significantly superior to placebo on all three measures of outcome.

(2) Study 2: The second study enrolled adult patients who met Research Diagnostic Criteria for manic disorder and who were hospitalized for acute mania. Depakote was initiated at a dose of 250 mg tid and adjusted within a dose range of 750-2,500 mg/day to achieve serum valproate concentrations in a range of 40-150 mcg/mL. Mean Depakote doses for completers in this study were 1,116, 1,683, and 2,006 mg/day at Days 7, 14, and 21, respectively. Study 2 also included a lithium group for which lithium doses for completers were 1,312, 1,869, and 1,984 mg/day at Days 7, 14, and 21, respectively. Patients were assessed on the Manic Rating Scale (MRS; score ranges from 11-63), and the primary outcome measures were the total MRS score, and scores for two subscales of the MRS, i.e., the Manic Syndrome Scale (MSS) and the Behavior and Ideation Scale (BIS). Baseline scores and change from baseline in the Week 3 endpoint (last-observation-carry-forward) analysis were as follows:

Table 7. Study 2
MRS Total Score
Group | Baseline^1 | BL to Day 21^2 | Difference^3
Placebo | 38.9 | - 4.4
Lithium | 37.9 | -10.5 | 6.1
Depakote | 38.1 | - 9.5 | 5.1
MSS Total Score
Group | Baseline^1 | BL to Day 21^2 | Difference^3
Placebo | 18.9 | - 2.5
Lithium | 18.5 | - 6.2 | 3.7
Depakote | 18.9 | - 6.0 | 3.5
BIS Total Score
Group | Baseline^1 | BL to Day 21^2 | Difference^3
Placebo | 16.4 | - 1.4
Lithium | 16.0 | - 3.8 | 2.4
Depakote | 15.7 | - 3.2 | 1.8
^1 Mean score at baseline
^2 Change from baseline to Day 21 (LOCF)
^3 Difference in change from baseline to Day 21 endpoint (LOCF) between Depakote and placebo and lithium and placebo

Depakote was statistically significantly superior to placebo on all three measures of outcome. An exploratory analysis for age and gender effects on outcome did not suggest any differential responsiveness on the basis of age or gender.

A comparison of the percentage of patients showing ≥ 30% reduction in the symptom score from baseline in each treatment group, separated by study, is shown in Figure 1.

Figure 1

* p < 0.05

PBO = placebo, DVPX = Depakote

14.2 Epilepsy

The efficacy of valproate in reducing the incidence of complex partial seizures (CPS) that occur in isolation or in association with other seizure types was established in two controlled trials.

In one, multi-clinic, placebo controlled study employing an add-on design (adjunctive therapy), 144 patients who continued to suffer eight or more CPS per 8 weeks during an 8 week period of monotherapy with doses of either carbamazepine or phenytoin sufficient to assure plasma concentrations within the "therapeutic range" were randomized to receive, in addition to their original antiepilepsy drug (AED), either Depakote or placebo. Randomized patients were to be followed for a total of 16 weeks. The following table presents the findings.

Table 8. Adjunctive Therapy Study Median Incidence of CPS per 8 Weeks
Add-on Treatment | Number of Patients | Baseline Incidence | Experimental Incidence
Depakote | 75 | 16.0 | 8.9*
Placebo | 69 | 14.5 | 11.5
* Reduction from baseline statistically significantly greater for valproate than placebo at p ≤ 0.05 level.

Figure 2 presents the proportion of patients (X axis) whose percentage reduction from baseline in complex partial seizure rates was at least as great as that indicated on the Y axis in the adjunctive therapy study. A positive percent reduction indicates an improvement (i.e., a decrease in seizure frequency), while a negative percent reduction indicates worsening. Thus, in a display of this type, the curve for an effective treatment is shifted to the left of the curve for placebo. This figure shows that the proportion of patients achieving any particular level of improvement was consistently higher for valproate than for placebo. For example, 45% of patients treated with valproate had a ≥ 50% reduction in complex partial seizure rate compared to 23% of patients treated with placebo.

Figure 2

The second study assessed the capacity of valproate to reduce the incidence of CPS when administered as the sole AED. The study compared the incidence of CPS among patients randomized to either a high or low dose treatment arm. Patients qualified for entry into the randomized comparison phase of this study only if 1) they continued to experience 2 or more CPS per 4 weeks during an 8 to 12 week long period of monotherapy with adequate doses of an AED (i.e., phenytoin, carbamazepine, phenobarbital, or primidone) and 2) they made a successful transition over a two week interval to valproate. Patients entering the randomized phase were then brought to their assigned target dose, gradually tapered off their concomitant AED and followed for an interval as long as 22 weeks. Less than 50% of the patients randomized, however, completed the study. In patients converted to Depakote monotherapy, the mean total valproate concentrations during monotherapy were 71 and 123 mcg/mL in the low dose and high dose groups, respectively.

The following table presents the findings for all patients randomized who had at least one post-randomization assessment.

Table 9. Monotherapy Study Median Incidence of CPS per 8 Weeks
Treatment | Number of Patients | Baseline Incidence | Randomized Phase Incidence
High dose Depakote | 131 | 13.2 | 10.7*
Low dose Depakote | 134 | 14.2 | 13.8
* Reduction from baseline statistically significantly greater for high dose than low dose at p ≤ 0.05 level.

Figure 3 presents the proportion of patients (X axis) whose percentage reduction from baseline in complex partial seizure rates was at least as great as that indicated on the Y axis in the monotherapy study. A positive percent reduction indicates an improvement (i.e., a decrease in seizure frequency), while a negative percent reduction indicates worsening. Thus, in a display of this type, the curve for a more effective treatment is shifted to the left of the curve for a less effective treatment. This figure shows that the proportion of patients achieving any particular level of reduction was consistently higher for high dose valproate than for low dose valproate. For example, when switching from carbamazepine, phenytoin, phenobarbital or primidone monotherapy to high dose valproate monotherapy, 63% of patients experienced no change or a reduction in complex partial seizure rates compared to 54% of patients receiving low dose valproate.

Figure 3

Information on pediatric studies is presented in section 8.

14.3 Migraine

The results of two multicenter, randomized, double-blind, placebo-controlled clinical trials established the effectiveness of Depakote in the prophylactic treatment of migraine headache.

Both studies employed essentially identical designs and recruited patients with a history of migraine with or without aura (of at least 6 months in duration) who were experiencing at least 2 migraine headaches a month during the 3 months prior to enrollment. Patients with cluster headaches were excluded. Women of childbearing potential were excluded entirely from one study, but were permitted in the other if they were deemed to be practicing an effective method of contraception.

In each study following a 4-week single-blind placebo baseline period, patients were randomized, under double blind conditions, to Depakote or placebo for a 12-week treatment phase, comprised of a 4-week dose titration period followed by an 8-week maintenance period. Treatment outcome was assessed on the basis of 4-week migraine headache rates during the treatment phase.

In the first study, a total of 107 patients (24 M, 83 F), ranging in age from 26 to 73 were randomized 2:1, Depakote to placebo. Ninety patients completed the 8-week maintenance period. Drug dose titration, using 250 mg tablets, was individualized at the investigator's discretion. Adjustments were guided by actual/sham trough total serum valproate levels in order to maintain the study blind. In patients on Depakote doses ranged from 500 to 2,500 mg a day. Doses over 500 mg were given in three divided doses (TID). The mean dose during the treatment phase was 1,087 mg/day resulting in a mean trough total valproate level of 72.5 mcg/mL, with a range of 31 to 133 mcg/mL.

The mean 4-week migraine headache rate during the treatment phase was 5.7 in the placebo group compared to 3.5 in the Depakote group (see Figure 4). These rates were significantly different.

In the second study, a total of 176 patients (19 males and 157 females), ranging in age from 17 to 76 years, were randomized equally to one of three Depakote dose groups (500, 1,000, or 1,500 mg/day) or placebo. The treatments were given in two divided doses (BID). One hundred thirty-seven patients completed the 8-week maintenance period. Efficacy was to be determined by a comparison of the 4-week migraine headache rate in the combined 1,000/1,500 mg/day group and placebo group.

The initial dose was 250 mg daily. The regimen was advanced by 250 mg every 4 days (8 days for 500 mg/day group), until the randomized dose was achieved. The mean trough total valproate levels during the treatment phase were 39.6, 62.5, and 72.5 mcg/mL in the Depakote 500, 1,000, and 1,500 mg/day groups, respectively.

The mean 4-week migraine headache rates during the treatment phase, adjusted for differences in baseline rates, were 4.5 in the placebo group, compared to 3.3, 3.0, and 3.3 in the Depakote 500, 1,000, and 1,500 mg/day groups, respectively, based on intent-to-treat results (see Figure 4). Migraine headache rates in the combined Depakote 1,000/1,500 mg group were significantly lower than in the placebo group.

Figure 4 Mean 4-week Migraine Rates

1 Mean dose of Depakote was 1,087 mg/day.

2 Dose of Depakote was 500 or 1,000 mg/day.

15 REFERENCES

1. Meador KJ, Baker GA, Browning N, et al. Fetal antiepileptic drug exposure and cognitive outcomes at age 6 years (NEAD study): a prospective observational study. Lancet Neurology 2013; 12 (3):244-252.

16 HOW SUPPLIED/STORAGE AND HANDLING

Depakote tablets (divalproex sodium delayed-release tablets) are supplied as:

125 mg salmon pink-colored tablets:

- Bottles of 100, tablets with the “a” logo and the code NT – NDC 0074-6212-13
- Bottles of 100, tablets with the code NT – NDC 0074-7325-13

250 mg peach-colored tablets:

- Bottles of 100, tablets with the “a” logo and the code NR – NDC 0074-6214-13
- Bottles of 100, tablets with the code NR – NDC 0074-7326-13

500 mg lavender-colored tablets:

- Bottles of 100, tablets with the “a” logo and the code NS – NDC 0074-6215-13
- Bottles of 100, tablets with the code NS – NDC 0074-7327-13

Recommended Storage: Store tablets below 86°F (30°C).

17 PATIENT COUNSELING INFORMATION

Advise the patient to read the FDA-approved patient labeling (Medication Guide).

Hepatotoxicity

Warn patients and guardians that nausea, vomiting, abdominal pain, anorexia, diarrhea, asthenia, and/or jaundice can be symptoms of hepatotoxicity and, therefore, require further medical evaluation promptly [see Warnings and Precautions (5.1)].

Pancreatitis

Warn patients and guardians that abdominal pain, nausea, vomiting, and/or anorexia can be symptoms of pancreatitis and, therefore, require further medical evaluation promptly [see Warnings and Precautions (5.5)].

Birth Defects and Decreased IQ

Inform pregnant women and women of childbearing potential (including girls beginning the onset of puberty) that use of valproate during pregnancy increases the risk of birth defects, decreased IQ, and neurodevelopmental disorders in children who were exposed in utero. Advise women to use effective contraception while taking valproate. When appropriate, counsel these patients about alternative therapeutic options. This is particularly important when valproate use is considered for a condition not usually associated with permanent injury or death such as prophylaxis of migraine headache [see Contraindications (4)]. Advise patients to read the Medication Guide, which appears as the last section of the labeling [see Warnings and Precautions (5.2, 5.3, 5.4) and Use in Specific Populations (8.1)].

Pregnancy Registry

Advise women of childbearing potential to discuss pregnancy planning with their doctor and to contact their doctor immediately if they think they are pregnant.

Encourage women who are taking Depakote to enroll in the North American Antiepileptic Drug (NAAED) Pregnancy Registry if they become pregnant. This registry is collecting information about the safety of antiepileptic drugs during pregnancy. To enroll, patients can call the toll free number 1-888-233-2334 or visit the website, http://www.aedpregnancyregistry.org/ [see Use in Specific Populations (8.1)].

Suicidal Thinking and Behavior

Counsel patients, their caregivers, and families that AEDs, including Depakote, may increase the risk of suicidal thoughts and behavior and to be alert for the emergence or worsening of symptoms of depression, any unusual changes in mood or behavior, or the emergence of suicidal thoughts, behavior, or thoughts about self-harm. Instruct patients, caregivers, and families to report behaviors of concern immediately to the healthcare providers [see Warnings and Precautions (5.7)].

Hyperammonemia

Inform patients of the signs and symptoms associated with hyperammonemic encephalopathy and to notify the prescriber if any of these symptoms occur [see Warnings and Precautions (5.9, 5.10)].

CNS Depression

Since valproate products may produce CNS depression, especially when combined with another CNS depressant (e.g., alcohol), advise patients not to engage in hazardous activities, such as driving an automobile or operating dangerous machinery, until it is known that they do not become drowsy from the drug.

Drug Reaction with Eosinophilia and Systemic Symptoms (DRESS)/Multiorgan Hypersensitivity Reactions

Instruct patients that a fever associated with other organ system involvement (rash, lymphadenopathy, etc.) may be drug-related. Advise patients to report such reactions to a healthcare provider immediately [see Warnings and Precautions (5.12)].

Serious Dermatologic Reactions

Advise patients of the early signs and symptoms of severe cutaneous adverse reactions and to report any occurrence immediately to a healthcare provider [see Warnings and Precautions (5.13)].

Angioedema

Advise patients to discontinue Depakote and seek immediate medical care if they develop signs or symptoms of angioedema, such as facial, perioral, or upper airway swelling [see Warnings and Precautions (5.14)].

Medication Residue in the Stool

Instruct patients to notify their healthcare provider if they notice a medication residue in the stool [see Warnings and Precautions (5.20)].

©1983-2025 AbbVie Inc.

20091022 R1

Mfd. by
AbbVie LTD,
Barceloneta, PR 00617

For
AbbVie Inc.,
North Chicago, IL 60064, U.S.A.

MEDICATION GUIDE
DEPAKOTE ER (dep-a-kOte)
(divalproex sodium)
Extended-Release Tablets, for oral use
DEPAKOTE (dep-a-kOte)
(divalproex sodium)
Delayed-Release Tablets, for oral use
DEPAKOTE Sprinkle Capsules (dep-a-kOte)
(divalproex sodium delayed release capsules)
for oral use

What is the most important information I should know about DEPAKOTE?
Do not stop Depakote without first talking to a healthcare provider. Stopping Depakote suddenly can cause serious problems. Stopping a seizure medicine suddenly in a patient who has epilepsy can cause seizures that will not stop (status epilepticus).
Depakote can cause serious side effects, including:
1. Serious liver damage that can cause death, especially in children younger than 2 years old and patients with mitochondrial disorders. The risk of getting this serious liver damage is more likely to happen within the first 6 months of treatment.
Call your healthcare provider right away if you get any of the following symptoms:

- feeling very weak, tired, or uncomfortable (malaise)
- swelling of your face
- not feeling hungry
- nausea or vomiting that does not go away
- diarrhea
- pain on the right side of your stomach (abdomen)
- dark urine
- yellowing of your skin or the whites of your eyes
- loss of seizure control in people with epilepsy

In some cases, liver damage may continue even though the medicine is stopped. Your healthcare provider will do blood tests to check your liver before and during treatment with DEPAKOTE.
2. Depakote may harm your unborn baby.

- If you take Depakote during pregnancy for any medical condition, your baby is at risk for serious birth defects that affect the brain and spinal cord (such as spina bifida or neural tube defects). These defects can begin in the first month, even before you know you are pregnant. Other birth defects that affect the structures of the heart, head, arms, legs, and the opening where the urine comes out (urethra) on the bottom of the penis can also happen. Decreased hearing or hearing loss can also happen.
- Birth defects may occur even in children born to women who are not taking any medicines and do not have other risk factors.
- Taking folic acid supplements before getting pregnant and during early pregnancy can lower the chance of having a baby with a neural tube defect.
- If you take Depakote during pregnancy for any medical condition, your child is at risk for having lower IQ and may be at risk for developing autism or attention deficit/hyperactivity disorder.
- There may be other medicines to treat your condition that have a lower chance of causing birth defects, decreased IQ, or other disorders in your child.
- Women who are pregnant must not take Depakote to prevent migraine headaches.
- All women of childbearing age (including girls from the start of puberty) should talk to their healthcare provider about using other possible treatments instead of Depakote. If the decision is made to use Depakote, you should use effective birth control (contraception).
- Tell your healthcare provider right away if you become pregnant while taking Depakote. You and your healthcare provider should decide if you will continue to take Depakote while you are pregnant.
- Pregnancy Registry: If you become pregnant while taking Depakote, talk to your healthcare provider about registering with the North American Antiepileptic Drug (NAAED) Pregnancy Registry. You can enroll in this registry by calling toll-free 1-888-233-2334 or by visiting the website, http://www.aedpregnancyregistry.org/. The purpose of this registry is to collect information about the safety of antiepileptic drugs during pregnancy.

3. Swelling (Inflammation) and bleeding (hemorrhaging) of your pancreas that can cause death.
Call your healthcare provider right away if you have any of these symptoms:

- severe stomach pain that you may also feel in your back
- nausea or vomiting that does not go away
- not feeling hungry

4. Like other antiepileptic drugs, Depakote may cause suicidal thoughts or actions in a very small number of people, about 1 in 500.
Call a healthcare provider right away if you have any of these symptoms, especially if they are new, worse, or worry you:

- thoughts about suicide or dying
- suicide attempt
- new or worse depression
- new or worse anxiety
- feeling agitated or restless
- panic attacks
- trouble sleeping (insomnia)
- new or worse irritability
- acting aggressive, being angry, or violent
- acting on dangerous impulses
- an extreme increase in activity and talking (mania)
- other unusual changes in behavior or mood

How can I watch for early symptoms of suicidal thoughts and actions?

- Pay attention to any changes, especially sudden changes in mood, behaviors, thoughts, or feelings.
- Keep all follow-up visits with your healthcare provider as scheduled.

Call your healthcare provider between visits as needed, especially if you are worried about symptoms.
Suicidal thoughts or actions can be caused by things other than medicines. If you have suicidal thoughts or actions, your healthcare provider may check for other causes.

What is Depakote?
Depakote ER tablets, Depakote delayed-release tablets, and Depakote Sprinkle Capsules are prescription medicines used:

- alone or with other medicines to treat:
  - complex partial seizures in adults and children 10 years of age and older
  - simple and complex absence seizures
- with other medications to treat:
  - patients with multiple seizure types that include absence seizures

Depakote ER tablets and Depakote delayed-release tablets are also used to prevent migraine headaches.
Depakote ER tablets are also used to treat acute manic or mixed episodes associated with bipolar disorder with or without psychotic features.
Depakote delayed-release tablets are also used to treat manic episodes associated with bipolar disorder.

Do not take Depakote if you:

- have liver problems.
- have or think you have a genetic liver problem caused by a mitochondrial disorder such as Alpers-Huttenlocher syndrome.
- are allergic to divalproex sodium, valproic acid, sodium valproate, or any of the ingredients in Depakote. See the end of this Medication Guide for a complete list of ingredients in Depakote.
- have a genetic problem called a urea cycle disorder.
- are taking it to prevent migraine headaches and are either pregnant or may become pregnant because you are not using effective birth control (contraception).

Before taking Depakote, tell your healthcare provider about all of your medical conditions including if you:

- have or have had liver problems.
- have or think you have a genetic liver problem caused by a mitochondrial disorder such as Alpers-Huttenlocher syndrome.
- drink alcohol.
- have or have had depression, suicidal thoughts or behavior, unusual changes in mood, or thoughts about self-harm.
- are male and plan to father a child. DEPAKOTE may cause fertility problems, which may affect your ability to father a child. Talk to your healthcare provider if this is a problem for you.
- are pregnant or may become pregnant. DEPAKOTE may harm your unborn baby. See “2. Depakote may harm your unborn baby” above for more information.
- are breastfeeding. Depakote can pass into breast milk and may harm your baby. Talk to your healthcare provider about the best way to feed your baby if you take Depakote.

Tell your healthcare provider about all the medicines you take, including prescription and over-the-counter medicines, vitamins, and herbal supplements.
DEPAKOTE may affect the way other medicines work, and other medicines may affect how DEPAKOTE works. Using DEPAKOTE with other medicines can cause serious side effects. Do not start or stop other medicines without talking to your healthcare provider.
Especially tell your healthcare provider if you take:

- medicines that can affect how the liver breaks down other medicines (such as phenytoin, carbamazepine, felbamate, phenobarbital, primidone, rifampin)
- aspirin, carbapenem antibiotics, or estrogen-containing hormonal contraceptives
- methotrexate
- topiramate
- cannabidiol

You can ask your healthcare provider or pharmacist for a list of these medicines if you are not sure.
Know the medicines you take. Keep a list of them and show it to your healthcare provider and pharmacist each time you get a new medicine.

How should I take Depakote?

- Depakote comes in different dosage forms.
- Take Depakote exactly as your healthcare provider tells you. Your healthcare provider will tell you how much Depakote to take and when to take it.
- Your healthcare provider may change your dose, if needed.
- Do not change your dose of Depakote without talking to your healthcare provider.
- Do not stop taking Depakote without first talking to your healthcare provider. Stopping Depakote suddenly can cause serious problems. See “What is the most important information I should know about Depakote?”.
- Swallow Depakote ER tablets or DEPAKOTE delayed-release tablets whole. Do not crush or chew them. Tell your healthcare provider if you cannot swallow Depakote ER tablets or DEPAKOTE delayed-release tablets whole. You may need a different medicine.
- Depakote Sprinkle Capsules may be swallowed whole, or the capsule may be opened and the contents may be mixed into a small amount of soft food, such as applesauce or pudding. See the Instructions for Use that comes with this Medication Guide for detailed instructions on how to use Depakote Sprinkle Capsules.
- If you miss a dose of DEPAKOTE ER tablets or DEPAKOTE delayed-release tablets, take it as soon as you remember unless it’s almost time for your next dose. Take the next dose at your regular time. Do not take 2 doses at the same time.
- If you take too much DEPAKOTE, call your healthcare provider or poison control center right away.

What should I avoid while taking Depakote?

- Do not drink alcohol while taking Depakote. Depakote and alcohol can affect each other causing side effects such as sleepiness and dizziness.
- Do not drive a car, operate dangerous machinery, or do dangerous activities until you know how Depakote affects you. Depakote can slow your thinking and motor skills and may affect your vision.

What are the possible side effects of Depakote?
Call your healthcare provider right away if you have any of the symptoms listed below. Your healthcare provider may do additional tests before and during your treatment with DEPAKOTE. Your healthcare provider may reduce your dose, temporarily stop, or permanently stop treatment if you have certain side effects.
Depakote can cause serious side effects including:

- See “What is the most important information I should know about Depakote?”
- bleeding problems. Call your healthcare provider if you have any symptoms of bleeding, including:

- bruising or red or purple spots on your skin

- vomiting blood or vomit that looks like coffee grounds

- bleeding from your mouth or nose

- blood in your stools or black stools (looks like tar)

- cough up blood or blood clots

- pain and swelling in your joints

- increased ammonia levels in your blood. High ammonia levels can seriously affect your mental activities, slow your alertness, make you feel tired, or cause vomiting (encephalopathy). This has happened when DEPAKOTE is taken alone or with a medicine called topiramate. Call your health care provider if you have any of these symptoms.
- low body temperature (hypothermia). A drop in your body temperature to less than 95°F can happen during treatment with DEPAKOTE. Call your healthcare provider if you have any of the following symptoms:

- feeling tired

- drowsiness

- confusion

- coma

- memory loss

- shivering

- severe multiorgan or skin reactions. Treatment with DEPAKOTE may cause serious or life-threatening allergic reactions that may affect your skin or other parts of your body. Stop taking DEPAKOTE, and contact your healthcare provider or get medical help right away, if you develop any of these symptoms:

- skin rash

- swelling of your lymph nodes

- hives

- swelling of your face, eyes, lips, tongue, or throat

- blistering and peeling of your skin

- trouble swallowing or breathing

- sores in your mouth

- drowsiness or sleepiness in the elderly. This extreme drowsiness may cause you to eat or drink less than you normally would. Tell your healthcare provider if you are not able to eat or drink as you normally do. Your healthcare provider may start you at a lower dose of Depakote.
- medicine residue in your stool. Tell your healthcare provider if you have or think you may have medicine residue in your stool.

The common side effects of DEPAKOTE include:

- headache

- low blood platelet count

- weakness

- stomach burning, fullness, or bloating after eating

- sleepiness

- nausea

- dizziness

- vomiting

- tremors

- stomach pain

- difficulty falling or staying asleep

- diarrhea

- double vision

- infection

- hair loss (alopecia)

These are not all of the possible side effects of Depakote.
Call your doctor for medical advice about side effects. You may report side effects to FDA at 1-800-FDA-1088.

How should I store Depakote?

- Store Depakote ER Tablets at room temperature between 68°F to 77°F (20°C to 25°C).
- Store Depakote delayed release tablets below 86°F (30°C).
- Store Depakote Sprinkle Capsules below 77°F (25°C).

Keep Depakote and all medicines out of the reach of children.

General information about the safe and effective use of Depakote
Medicines are sometimes prescribed for purposes other than those listed in a Medication Guide. Do not use Depakote for a condition for which it was not prescribed. Do not give Depakote to other people, even if they have the same symptoms that you have. It may harm them.
You can ask your pharmacist or healthcare provider for information about Depakote that is written for health professionals.

What are the ingredients in Depakote?
Active ingredient: divalproex sodium
Inactive ingredients:

- Depakote ER tablets: FD&C Blue No. 1, hypromellose, lactose, microcrystalline cellulose, polyethylene glycol, potassium sorbate, propylene glycol, silicon dioxide, titanium dioxide, and triacetin. The 500 mg tablets also contain iron oxide and polydextrose.
- Depakote delayed-release tablets: cellulosic polymers, diacetylated monoglycerides, povidone, pregelatinized starch (contains corn starch), silica gel, talc, titanium dioxide, and vanillin.
  - Individual tablets also contain:
    125 mg tablets: FD&C Blue No. 1 and FD&C Red No. 40,
    250 mg tablets: FD&C Yellow No. 6 and iron oxide,
    500 mg tablets: D&C Red No. 30, FD&C Blue No. 2, and iron oxide.
- Depakote Sprinkle Capsules: cellulosic polymers, D&C Red No. 28, FD&C Blue No. 1 gelatin, iron oxide, magnesium stearate, silica gel, titanium dioxide, and triethyl citrate.

Manufactured by:
Depakote ER tablets:
250 mg is Mfd. by AbbVie LTD, Barceloneta, PR 00617
500 mg is Mfd. by AbbVie Inc., North Chicago, IL 60064 U.S.A. or
AbbVie LTD, Barceloneta, PR 00617
For AbbVie Inc., North Chicago, IL 60064 U.S.A.
Depakote delayed-release tablets:
Mfd. by AbbVie LTD, Barceloneta, PR 00617
For AbbVie Inc., North Chicago, IL 60064, U.S.A.
Depakote Sprinkle Capsules:
AbbVie Inc., North Chicago, IL 60064, U.S.A.
For more information, go to www.rxabbvie.com or call 1-800-633-9110.

This Medication Guide has been approved by the U.S. Food and Drug Administration. Revised: May 2025

©1983-2025 AbbVie Inc.

20091022 R1

PACKAGE LABEL

NDC 0074-6212-13

100 Tablets

DEPAKOTE®

DIVALPROEX SODIUM DELAYED-RELEASE TABLETS

125 mg Valproic Acid Activity

PACKAGE LABEL

NDC 0074-7325-13

100 Tablets

DEPAKOTE®

DIVALPROEX SODIUM DELAYED-RELEASE TABLETS

125 mg Valproic Acid Activity

Dispense the accompanying Medication Guide to each patient.

Rx only abbvie

PACKAGE LABEL

NDC 0074-6214-53

PACKAGE LABEL

NDC 0074-6214-13

100 Tablets

DEPAKOTE®

DIVALPROEX SODIUM DELAYED-RELEASE TABLETS

250 mg Valproic Acid Activity

PACKAGE LABEL

NDC 0074-6215-13

100 Tablets

DEPAKOTE®

DIVALPROEX SODIUM DELAYED-RELEASE TABLETS

500 mg Valproic Acid Activity

PACKAGE LABEL

NDC 0074-7327-13

100 Tablets

DEPAKOTE®

DIVALPROEX SODIUM DELAYED-RELEASE TABLETS

500 mg Valproic Acid Activity

Dispense the accompanying Medication Guide to each patient.

Rx only abbvie

PACKAGE LABEL

NDC 0074-7326-13

100 Tablets

DEPAKOTE®

DIVALPROEX SODIUM DELAYED-RELEASE TABLETS

250 mg Valproic Acid Activity

Do not accept if seal over bottle opening is broken or missing.

Dispense the accompanying Medication Guide to each patient.

Rx only abbvie